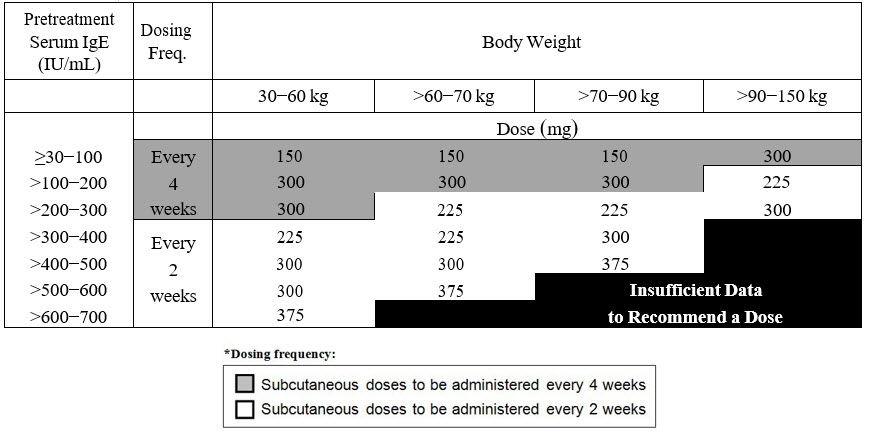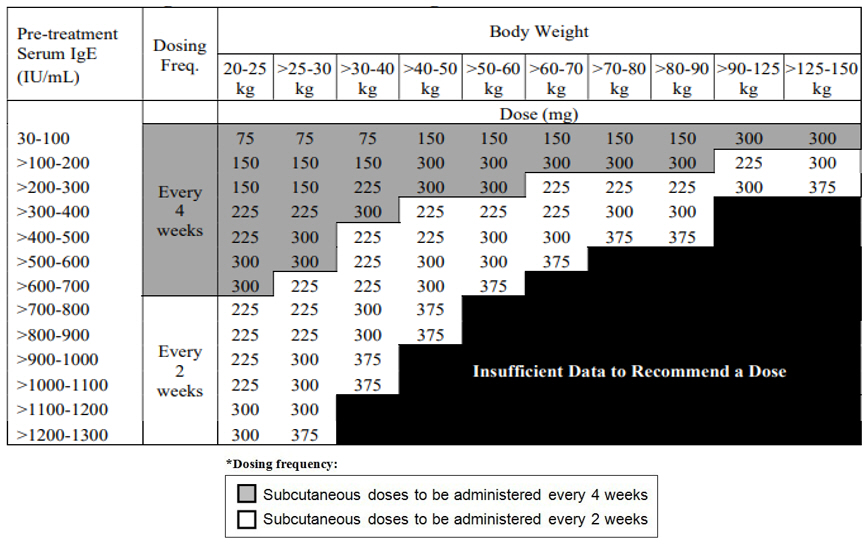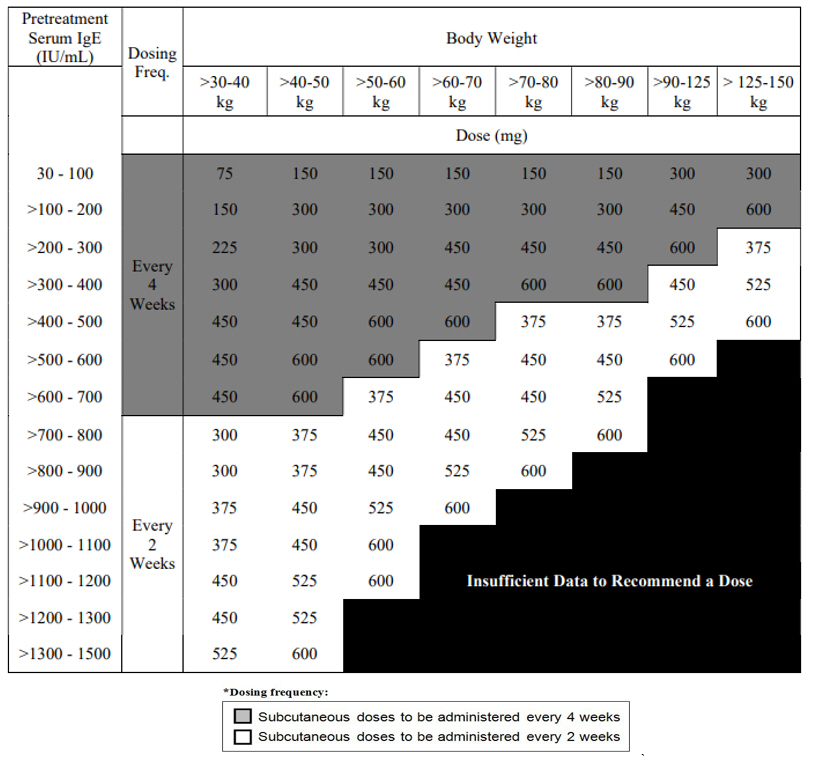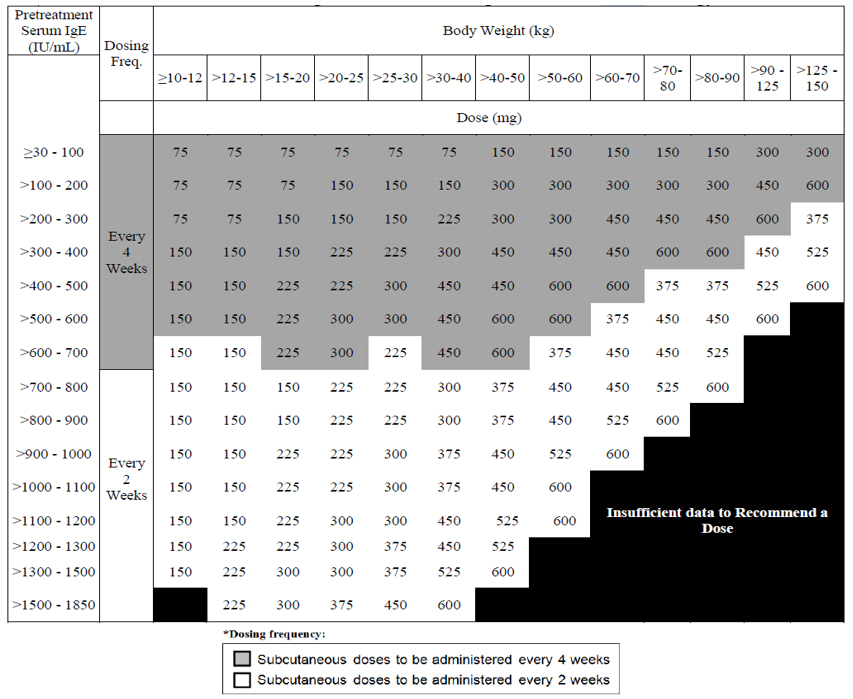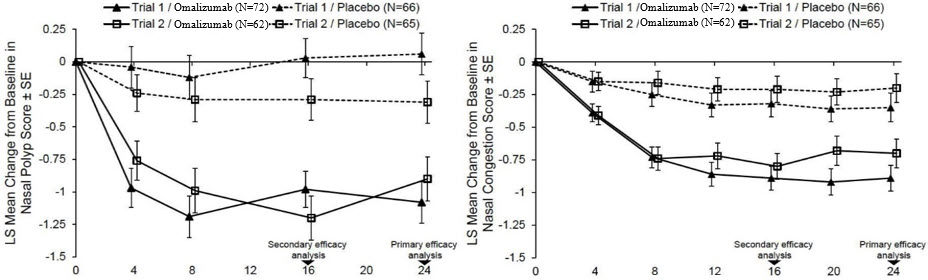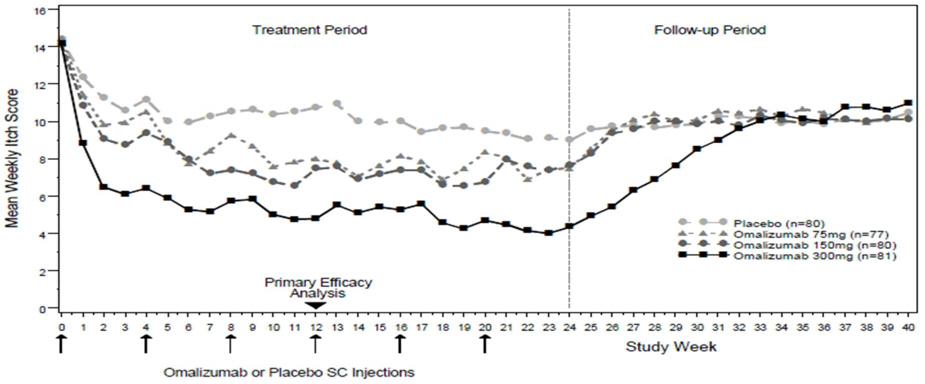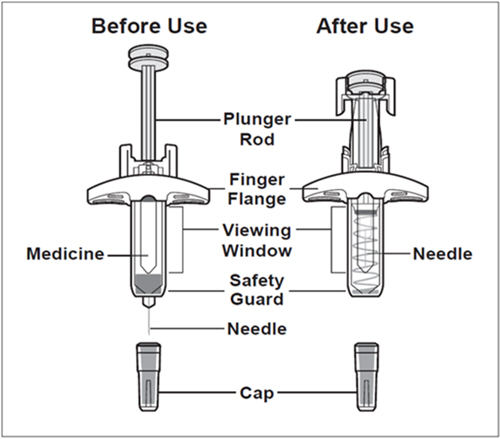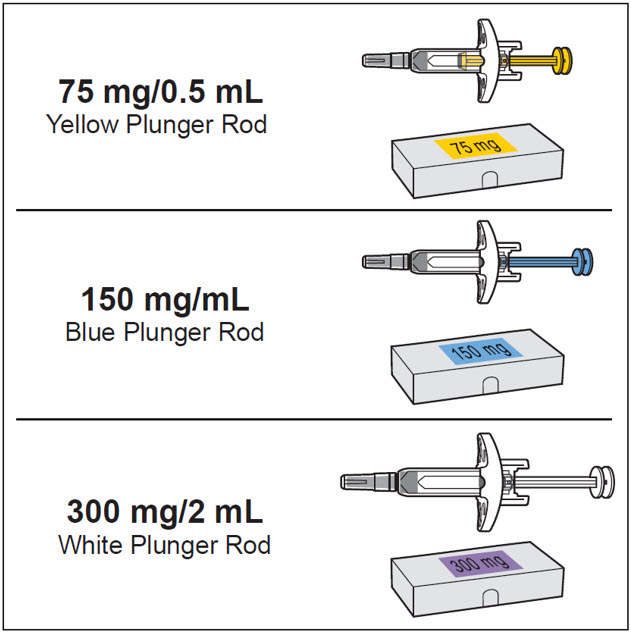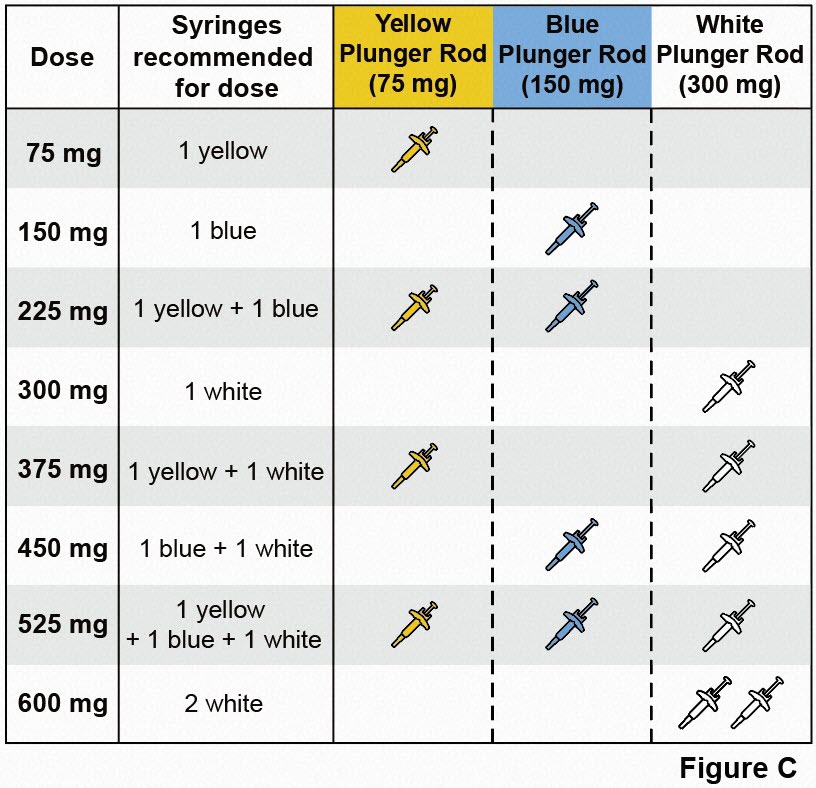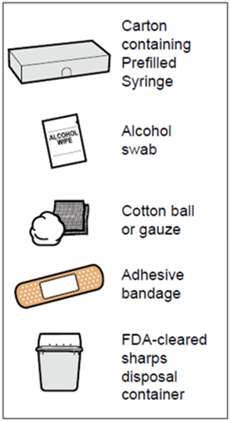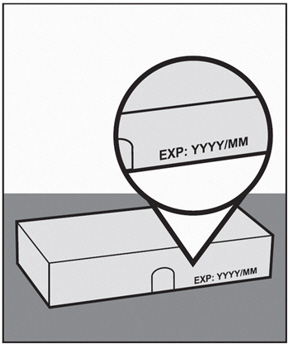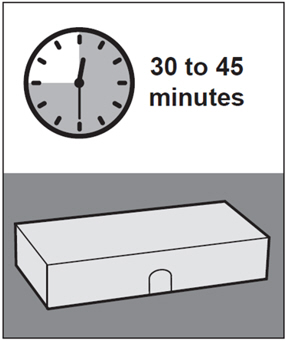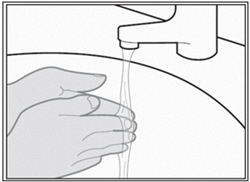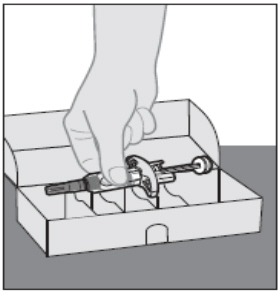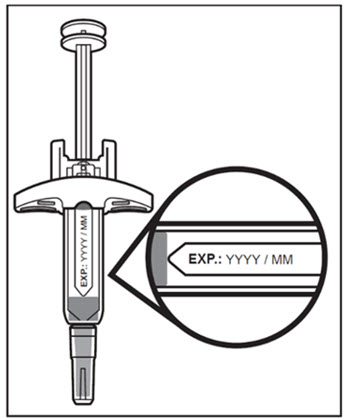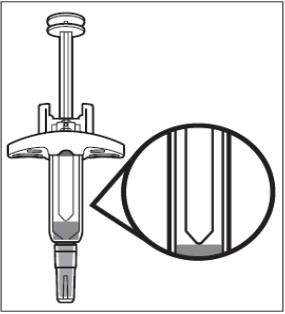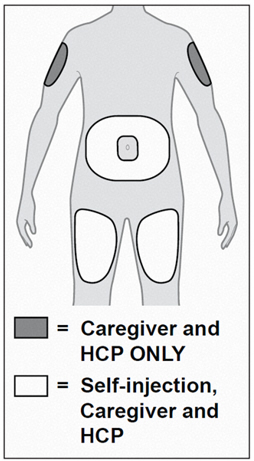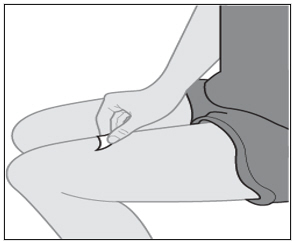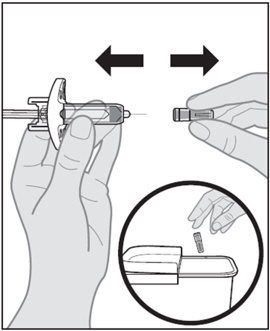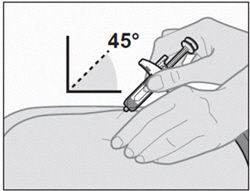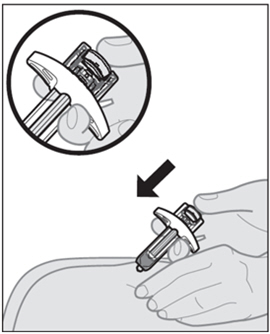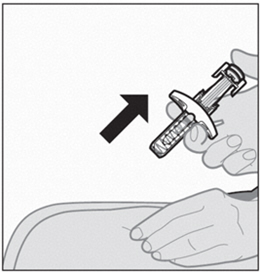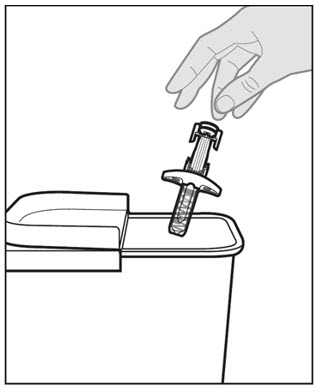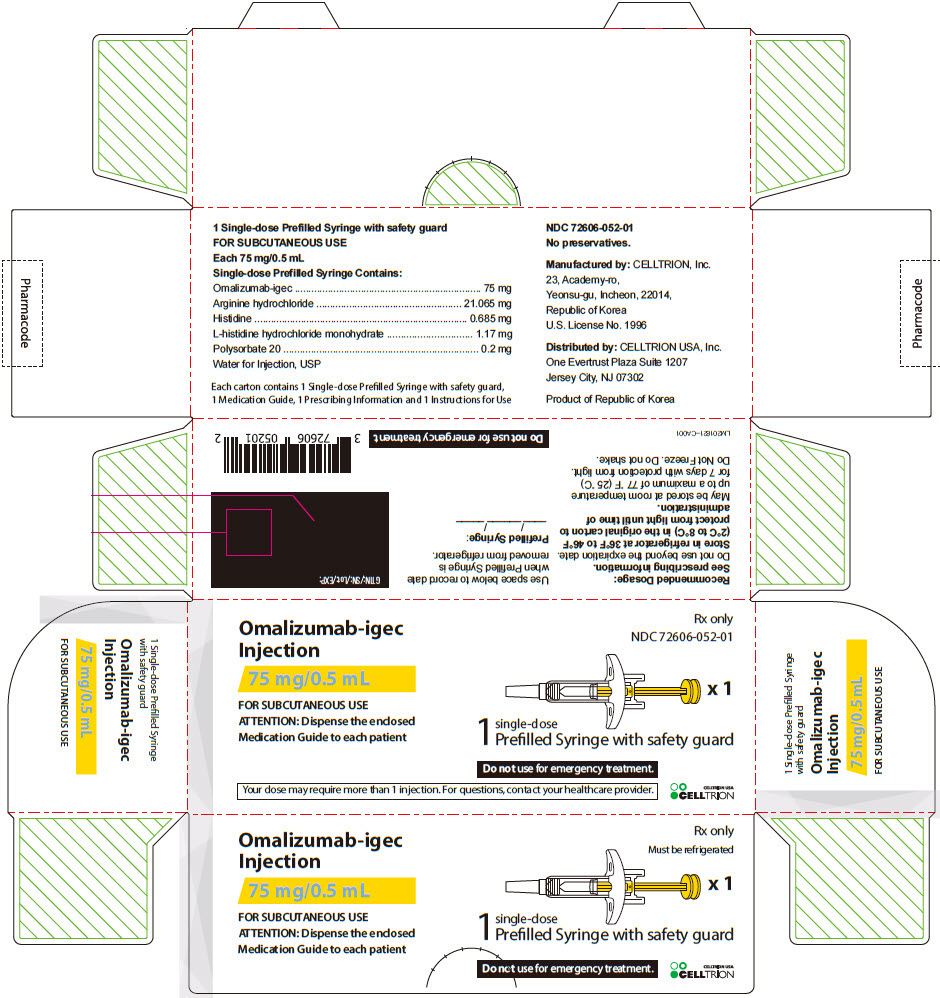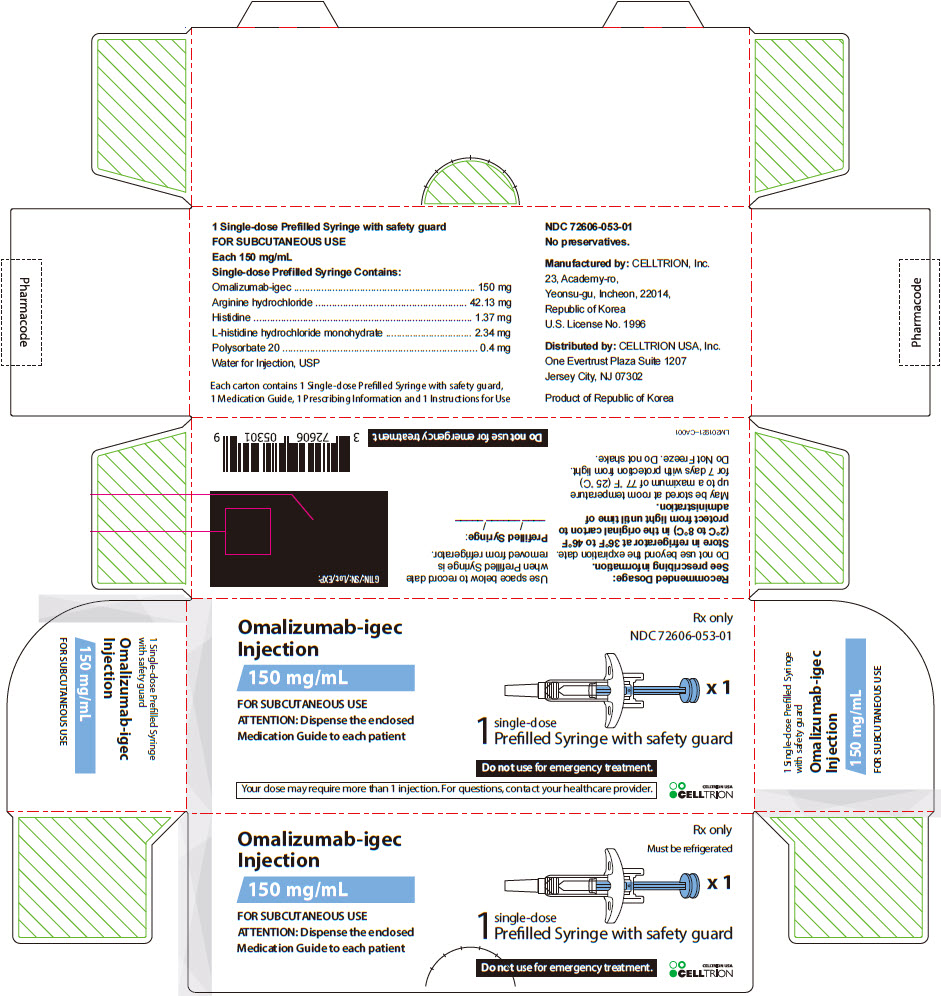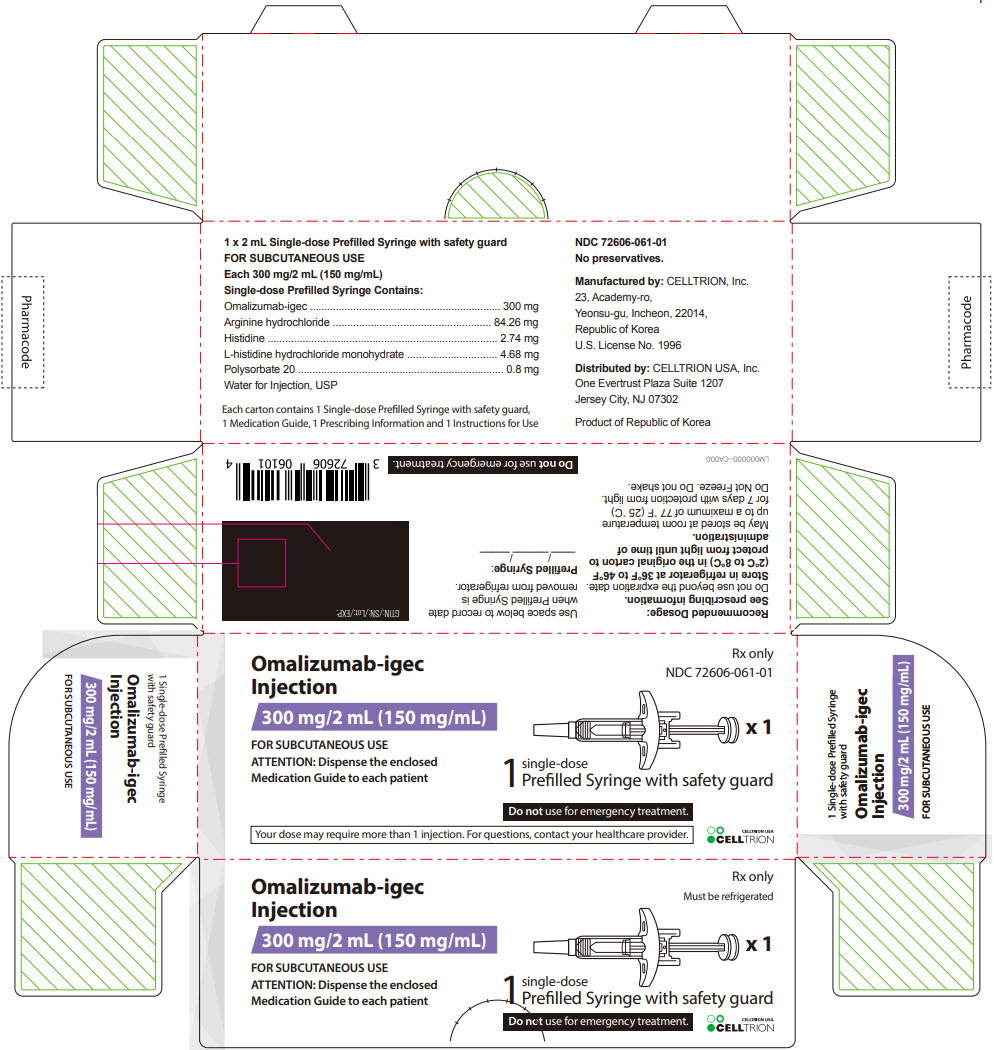 DRUG LABEL: Omalizumab-igec
NDC: 72606-052 | Form: INJECTION
Manufacturer: CELLTRION, Inc.
Category: prescription | Type: HUMAN PRESCRIPTION DRUG LABEL
Date: 20251205

ACTIVE INGREDIENTS: omalizumab 75 mg/0.5 mL
INACTIVE INGREDIENTS: ARGININE HYDROCHLORIDE 21.065 mg/0.5 mL; HISTIDINE 0.685 mg/0.5 mL; HISTIDINE MONOHYDROCHLORIDE MONOHYDRATE 1.17 mg/0.5 mL; POLYSORBATE 20 0.2 mg/0.5 mL; WATER

HIGHLIGHTS OF PRESCRIBING INFORMATION

These highlights do not include all the information needed to use OMALIZUMAB-IGEC safely and effectively. See full prescribing information for OMALIZUMAB-IGEC.
OMALIZUMAB-IGEC injection, for subcutaneous use
Initial U.S. Approval: 2025
Omalizumab-igec is biosimilar [Biosimilar means that the biological product is approved based on data demonstrating that it is highly similar to an FDA-approved biological product, known as a reference product and that there are no clinically meaningful differences between the biosimilar product and the reference product. Biosimilarity of Omalizumab-igec has been demonstrated for the condition(s) of use (e.g., indication(s) dosing regimen(s)), strength(s), dosage form(s), and route(s) of administration described in its Full Prescribing Information.] to XOLAIR® (omalizumab)

WARNING: ANAPHYLAXIS

See full prescribing information for complete boxed warning.

Anaphylaxis, presenting as bronchospasm, hypotension, syncope, urticaria, and/or angioedema of the throat or tongue, has been reported to occur after administration of omalizumab products. Anaphylaxis has occurred after the first dose of omalizumab products but also has occurred beyond 1 year after beginning treatment. Initiate Omalizumab-igec therapy in a healthcare setting, closely observe patients for an appropriate period of time after Omalizumab-igec administration and be prepared to manage anaphylaxis which can be life-threatening. Inform patients of the signs and symptoms of anaphylaxis and have them seek immediate medical care should symptoms occur. Selection of patients for self-administration of Omalizumab-igec should be based on criteria to mitigate risk from anaphylaxis. (2.6, 5.1, 6.1, 6.2)

RECENT MAJOR CHANGES

Dosage and Administration, Recommended Dosage for Chronic Spontaneous Urticaria (2.5) | 12/2025
Dosage and Administration, Omalizumab-igec Prefilled Syringe (2.7) | 12/2025

1 INDICATIONS AND USAGE

Omalizumab-igec is an anti-IgE antibody indicated for:

- Moderate to severe persistent asthma in adults and pediatric patients 6 years of age and older with a positive skin test or in vitro reactivity to a perennial aeroallergen and symptoms that are inadequately controlled with inhaled corticosteroids (1.1)
- Chronic rhinosinusitis with nasal polyps (CRSwNP) in adult patients 18 years of age and older with inadequate response to nasal corticosteroids, as add-on maintenance treatment (1.2)
- IgE-mediated food allergy in adult and pediatric patients aged 1 year and older for the reduction of allergic reactions (Type I), including anaphylaxis, that may occur with accidental exposure to one or more foods. To be used in conjunction with food allergen avoidance (1.3)
- Chronic spontaneous urticaria (CSU) in adults and adolescents 12 years of age and older who remain symptomatic despite H1 antihistamine treatment (1.4)

Limitations of Use:

- Not indicated for acute bronchospasm or status asthmaticus. (1.1, 5.3)
- Not indicated for the emergency treatment of allergic reactions, including anaphylaxis (1.3)
- Not indicated for other forms of urticaria. (1.4)

2 DOSAGE AND ADMINISTRATION

For subcutaneous (SC) administration only. (2.2, 2.3, 2.4, 2.5)

See full prescribing information for administration instructions (2.6, 2.7).

- Asthma: Omalizumab-igec 75 to 375 mg SC every 2 or 4 weeks. Determine dose (mg) and dosing frequency by serum total IgE level (IU/mL), measured before the start of treatment, and body weight (kg). See the dose determination charts. (2.2)
- Chronic Rhinosinusitis with Nasal Polyps: Omalizumab-igec 75 to 600 mg SC every 2 or 4 weeks. Determine dose (mg) and dosing frequency by serum total IgE level (IU/mL), measured before the start of treatment, and body weight (kg). See the dose determination charts. (2.3)
- IgE-Mediated Food Allergy: Omalizumab-igec 75 mg to 600 mg SC every 2 or 4 weeks. Determine dose (mg) and dosing frequency by serum total IgE level (IU/mL), measured before the start of treatment, and body weight (kg). See the dose determination chart. (2.4)
- Chronic Spontaneous Urticaria: Omalizumab-igec 150 or 300 mg SC every 4 weeks. Dosing in CSU is not dependent on serum IgE level or body weight. (2.5)

3 DOSAGE FORMS AND STRENGTHS

- Injection: 75 mg/0.5 mL, 150 mg/mL, and 300 mg/ 2 mL (150 mg/mL), solution in a single-dose prefilled syringe (3)

4 CONTRAINDICATIONS

Severe hypersensitivity reaction to omalizumab productsor any ingredient of Omalizumab-igec (4, 5.1)

5 WARNINGS AND PRECAUTIONS

- Anaphylaxis: Initiate Omalizumab-igec therapy in a healthcare setting prepared to manage anaphylaxis which can be life-threatening and observe patients for an appropriate period of time after administration. (5.1)
- Malignancy: Malignancies have been observed in clinical studies. (5.2)
- Acute Asthma Symptoms: Do not use for the treatment of acute bronchospasm or status asthmaticus. (5.3)
- Corticosteroid Reduction: Do not abruptly discontinue corticosteroids upon initiation of Omalizumab-igec therapy. (5.4)
- Eosinophilic Conditions: Be alert to eosinophilia, vasculitic rash, worsening pulmonary symptoms, cardiac complications, and/or neuropathy, especially upon reduction of oral corticosteroids. (5.5)
- Fever, Arthralgia, and Rash: Stop Omalizumab-igec if patients develop signs and symptoms similar to serum sickness. (5.6)
- Potential Medication Error Related to Emergency Treatment of Anaphylaxis: Omalizumab-igec should not be used for emergency treatment of allergic reactions, including anaphylaxis. (5.9)

6 ADVERSE REACTIONS

- Asthma: The most common adverse reactions (≥ 1% of patients) in clinical studies with adult and adolescent patients ≥12 years of age were arthralgia, pain (general), leg pain, fatigue, dizziness, fracture, arm pain, pruritus, dermatitis, and earache. In clinical studies with pediatric patients 6 to <12 years of age, the most common adverse reactions (≥ 3% of patients) were nasopharyngitis, headache, pyrexia, upper abdominal pain, pharyngitis streptococcal, otitis media, viral gastroenteritis, arthropod bites, and epistaxis. (6.1)
- Chronic Rhinosinusitis with Nasal Polyps: The most common adverse reactions (≥ 3% of patients) in clinical studies with adult patients included the following: headache, injection site reaction, arthralgia, upper abdominal pain, and dizziness. (6.1)
- IgE-Mediated Food Allergy: The most common adverse reactions (≥3% of patients) were injection site reactions and pyrexia. (6.1)
- Chronic Spontaneous Urticaria: The most common adverse reactions (≥2% of patients) included the following: nausea, nasopharyngitis, sinusitis, upper respiratory tract infection, viral upper respiratory tract infection, arthralgia, headache, and cough. (6.1)

To report SUSPECTED ADVERSE REACTIONS, contact CELLTRION USA, Inc. at 1-800-560-9414 or FDA at 1-800-FDA-1088 or www.fda.gov/medwatch.

7 DRUG INTERACTIONS

No formal drug interaction studies have been performed. (7)

FULL PRESCRIBING INFORMATION

WARNING: ANAPHYLAXIS

Anaphylaxis presenting as bronchospasm, hypotension, syncope, urticaria, and/or angioedema of the throat or tongue, has been reported to occur after administration of omalizumab products. Anaphylaxis has occurred as early as after the first dose of omalizumab products, but also has occurred beyond 1 year after beginning regularly administered treatment. Because of the risk of anaphylaxis, initiate Omalizumab-igec therapy in a healthcare setting and closely observe patients for an appropriate period of time after Omalizumab-igec administration. Health care providers administering Omalizumab-igec should be prepared to manage anaphylaxis which can be life-threatening. Inform patients of the signs and symptoms of anaphylaxis and instruct them to seek immediate medical care should symptoms occur. Selection of patients for self-administration of Omalizumab-igec should be based on criteria to mitigate risk from anaphylaxis [see Dosage and Administration (2.6), Warnings and Precautions (5.1) and Adverse Reactions (6.1, 6.2)].

1 INDICATIONS AND USAGE

1.1 Asthma

Omalizumab-igec is indicated for adults and pediatric patients 6 years of age and older with moderate to severe persistent asthma who have a positive skin test or in vitro reactivity to a perennial aeroallergen and whose symptoms are inadequately controlled with inhaled corticosteroids.

Limitations of Use:

Omalizumab-igec is not indicated for the relief of acute bronchospasm or status asthmaticus.

1.2 Chronic Rhinosinusitis with Nasal Polyps

Omalizumab-igec is indicated for add-on maintenance treatment of chronic rhinosinusitis with nasal polyps (CRSwNP) in adult patients 18 years of age and older with inadequate response to nasal corticosteroids.

1.3 IgE-Mediated Food Allergy

Omalizumab-igec is indicated for the reduction of allergic reactions (Type I), including anaphylaxis, that may occur with accidental exposure to one or more foods in adult and pediatric patients aged 1 year and older with IgE-mediated food allergy.

Omalizumab-igec is to be used in conjunction with food allergen avoidance.

Limitations of Use:

Omalizumab-igec is not indicated for the emergency treatment of allergic reactions, including anaphylaxis.

1.4 Chronic Spontaneous Urticaria

Omalizumab-igec is indicated for the treatment of adults and adolescents 12 years of age and older with chronic spontaneous urticaria (CSU) who remain symptomatic despite H1 antihistamine treatment.

Limitations of Use:

Omalizumab-igec is not indicated for treatment of other forms of urticaria.

2 DOSAGE AND ADMINISTRATION

2.1 Overview of Dosage Determination

Asthma, and Chronic Rhinosinusitis with Nasal Polyps, and IgE-Mediated Food Allergy

- Determine dosage of Omalizumab-igec by serum total IgE level (IU/mL) measured before the start of treatment, and by body weight (kg).
- For patients with asthma, chronic rhinosinusitis with nasal polyps (CRSwNP), and IgE-mediated food allergy, dosage determination should be based on the primary diagnosis for which Omalizumab-igec is being prescribed.
- Adjust doses for significant changes in body weight during treatment.
- Refer to Tables 1 and 2 for the recommended dosage for treatment of asthma, Table 3 for treatment of CRSwNP, and Table 4 for treatment of IgE-mediated food allergy.
- Total IgE levels are elevated during treatment and remain elevated for up to one year after the discontinuation of treatment. Therefore, re-testing of IgE levels during Omalizumab-igec treatment cannot be used as a guide for dose determination.
  - Interruptions lasting less than one year: Dose based on serum IgE levels obtained at the initial dose determination.
  - Interruptions lasting one year or more: Re-test total serum IgE levels for dose determination (Table 1 or 2 for treatment of asthma, based on the patient's age, Table 3 for treatment of CRSwNP, and Table 4 for treatment of IgE-mediated food allergy).

Chronic Spontaneous Urticaria

Dosage of Omalizumab-igec in patients with chronic spontaneous urticaria (CSU) is not dependent on serum IgE (free or total) level or body weight [see Dosage and Administration (2.5)].

2.2 Recommended Dosage for Asthma

The recommended dosage for asthma is Omalizumab-igec 75 mg to 375 mg by subcutaneous injection every 2 or 4 weeks based on serum total IgE level (IU/mL) measured before the start of treatment and by body weight (kg) [see Dosage and Administration (2.1)].

- Adult and adolescent patients 12 years of age and older: Initiate dosing according to Table 1.
- Pediatric patients 6 to <12 years of age: Initiate dosing according to Table 2.

Table 1. Subcutaneous Omalizumab-igec Doses Every 2 or 4 Weeks* for Patients 12 Years of Age and Older with Asthma

Table 2. Subcutaneous Omalizumab-igec Doses Every 2 or 4 Weeks* for Pediatric Patients with Asthma Who Begin Omalizumab-igec Between the Ages of 6 to <12 Years

Duration of Therapy

Periodically reassess the need for continued therapy based upon the patient's disease severity and level of asthma control.

2.3 Recommended Dosage for Chronic Rhinosinusitis with Nasal Polyps

The recommended dosage for chronic rhinosinusitis with nasal polyps (CRSwNP) is Omalizumab-igec 75 mg to 600 mg by subcutaneous injection every 2 or 4 weeks based on serum total IgE level (IU/mL) measure before the start of treatment and by body weight (kg) [see Dosage and Administration (2.1)]. Refer to Table 3 for recommended dosage based on serum total IgE level and body weight for patients with CRSwNP.

Table 3. Subcutaneous Omalizumab-igec Doses Every 2 or 4 Weeks* for Adult Patients with CRSwNP

Duration of Therapy

Periodically reassess the need for continued therapy based upon the patient's disease severity and level of symptom control.

2.4 Recommended Dosage for IgE-Mediated Food Allergy

The recommended dosage for IgE-mediated food allergy is Omalizumab-igec 75 mg to 600 mg by subcutaneous injection every 2 or 4 weeks based on serum total IgE level (IU/mL), measured before the start of treatment, and by body weight [see Dosage and Administration (2.1)].

Refer to Table 4 for recommended dosage based on serum IgE level and body weight for patients with IgE-mediated food allergy.

Table 4. Subcutaneous Omalizumab-igec Doses Every 2 or 4 Weeks* for Adult and Pediatric Patients 1 Year of Age and Older with IgE-Mediated Food Allergy

Duration of Therapy

The appropriate duration of therapy for IgE-mediated food allergy has not been evaluated. Periodically reassess the need for continued therapy.

2.5 Recommended Dosage for Chronic Spontaneous Urticaria

The recommended dosage for chronic spontaneous urticaria (CSU) is Omalizumab-igec 150 mg or 300 mg by subcutaneous injection every 4 weeks.

- The 300 mg dose may be administered as one subcutaneous injection of 300 mg/2 mL or as two subcutaneous injections of 150 mg/mL.
- Dosing of Omalizumab-igec in CSU patients is not dependent on serum IgE (free or total) level or body weight.

Duration of Therapy

The appropriate duration of therapy for CSU has not been evaluated. Periodically reassess the need for continued therapy.

2.6 Administration Overview

- Administer Omalizumab-igec by subcutaneous injection.
- Omalizumab-igec is intended for use under the guidance of a healthcare provider.
- Initiate therapy in a healthcare setting and once therapy has been safely established, the healthcare provider may determine whether self- administration of Omalizumab-igec prefilled syringe by the patient or caregiver is appropriate, based on careful assessment of risk for anaphylaxis and mitigation strategies.

Selection of Patients for Self-Administration of Omalizumab-igec Prefilled Syringe

Healthcare providers should consider known risk factors for anaphylaxis to Omalizumab-igec [see Warnings and Precautions (5.1)] and mitigation strategies when selecting patients for self-administration. Patient-specific factors including the following criteria should be considered:

1a) Asthma, CRSwNP and CSU: Patient should have no prior history of anaphylaxis to Omalizumab-igec or other agents, such as foods, drugs, biologics, etc.
1b) IgE-Mediated Food Allergy: Patient should have no prior history of anaphylaxis to Omalizumab-igec or other agents (except foods), such as drugs, biologics, etc.
2) Patient should receive at least 3 doses of Omalizumab-igec under the guidance of a healthcare provider with no hypersensitivity reactions
3) Patient or caregiver is able to recognize symptoms of anaphylaxis
4) Patient or caregiver is able to treat anaphylaxis appropriately
5) Patient or caregiver is able to perform subcutaneous injections with Omalizumab-igec prefilled syringe or autoinjector with proper technique according to the prescribed dosing regimen and Instructions for Use

2.7 Omalizumab-igec Prefilled Syringe

Omalizumab-igec injection doses are available as a prefilled syringe Instruct patients or caregivers to follow the directions provided in the "Instructions for Use" for preparation and administration of Omalizumab-igec Prefilled Syringe [see Instructions for Use].

- Adolescents 12 years of age and older: Omalizumab-igec prefilled syringe may be self-administered under adult supervision.
- Pediatric Patients 1 to 11 years of age: Omalizumab-igec prefilled syringe should be administered by a caregiver.

Administration Instructions for Prefilled Syringe

- Parenteral drug products should be inspected visually for particulate matter and discoloration prior to administration, whenever solution and container permit. Omalizumab-igec prefilled syringe solution should be clear to opalescent and colorless to pale brownish yellow. Do not use the prefilled syringe if the medicine is distinctly cloudy, discolored, or contains particles.
- Determine the number of prefilled syringes needed for patient's dosage (see Table 5). For pediatric patients 1 to 11 years of age, consideration should be given to the number of prefilled syringe injections needed and volume to be injected relative to the patient's bodyweight.
- For patients requiring more than 1 injection to complete a full dose, administer each injection at least 1-inch (2.5 cm) apart from other injection sites.
- Administer subcutaneous injection into the thigh or abdomen, avoiding the 2-inch (5 cm) area directly around the navel. The outer area of the upper arms may be used only if the injection is being given by a caregiver or healthcare provider [see Instructions for Use]. The injection may take up to 15 seconds to administer.

Table 5. Number of Omalizumab-igec Prefilled Syringes, Injections and Total Injection Volumes [This table represents the fewest number of injections for the patient, however, there are other syringe dosing combinations to achieve desired dose.]
Omalizumab-igec Dose [The 75 mg, 150 mg, 225 mg, 300 mg, and 375 mg Omalizumab-igec doses are approved for use in asthma patients. All doses in the table are approved for use in CRSwNP and IgE-mediated food allergy patients. The 150 mg and 300 mg Omalizumab-igec doses are also approved for use in CSU patients.] | 75 mg | 150 mg | 300 mg | Total Volume Injected
75 mg | 1 | 0 | 0 | 0.5 mL
150 mg | 0 | 1 | 0 | 1 mL
225 mg | 1 | 1 | 0 | 1.5 mL
300 mg | 0 | 0 | 1 | 2 mL
375 mg | 1 | 0 | 1 | 2.5 mL
450 mg | 0 | 1 | 1 | 3 mL
525 mg | 1 | 1 | 1 | 3.5 mL
600 mg | 0 | 0 | 2 | 4 mL

3 DOSAGE FORMS AND STRENGTHS

- Injection: 75 mg/0.5 mL is a clear to opalescent and colorless to pale brownish-yellow solution in a single-dose prefilled syringe with yellow plunger rod and safety guard.
- Injection: 150 mg/mL is a clear to opalescent and colorless to pale brownish-yellow solution in a single-dose prefilled syringe with blue plunger rod and safety guard.
- Injection: 300 mg/2 mL (150 mg/mL) is a clear to opalescent and colorless to pale brownish-yellow solution in a single-dose prefilled syringe with white plunger rod and safety guard

4 CONTRAINDICATIONS

Omalizumab-igec is contraindicated in patients with severe hypersensitivity reaction to omalizumab products or any ingredient of Omalizumab-igec [see Warnings and Precautions (5.1)].

5 WARNINGS AND PRECAUTIONS

5.1 Anaphylaxis

Anaphylaxis has been reported to occur after administration of omalizumab products in premarketing clinical trials and in postmarketing spontaneous reports [see Boxed Warning and Adverse Reactions (6.2)]. Signs and symptoms in these reported cases have included bronchospasm, hypotension, syncope, urticaria, and/or angioedema of the throat or tongue. Some of these events have been life-threatening. In premarketing clinical trials in patients with asthma, anaphylaxis was reported in 3 of 3,507 (0.1%) patients. Anaphylaxis occurred with the first dose of omalizumab in two patients and with the fourth dose in one patient. The time to onset of anaphylaxis was 90 minutes after administration in two patients and 2 hours after administration in one patient.

A case-control study in asthma patients showed that, among omalizumab users, patients with a history of anaphylaxis to foods, medications, or other causes were at increased risk of anaphylaxis associated with omalizumab products, compared to those with no prior history of anaphylaxis [see Adverse Reactions (6.1)].

In postmarketing spontaneous reports, the frequency of anaphylaxis attributed to omalizumab use was estimated to be at least 0.2% of patients based on an estimated exposure of 57,300 patients from June 2003 through December 2006. Anaphylaxis has occurred as early as after the first dose of omalizumab, but also has occurred beyond one year after beginning regularly scheduled treatment. Approximately 60% to 70% of anaphylaxis cases have been reported to occur within the first three doses of omalizumab, with additional cases occurring sporadically beyond the third dose.

Initiate Omalizumab-igec only in a healthcare setting equipped to manage anaphylaxis, which can be life-threatening. Observe patients closely for an appropriate period of time after administration of Omalizumab-igec, taking into account the time to onset of anaphylaxis seen in premarketing clinical trials and postmarketing spontaneous reports [see Adverse Reactions (6.1, 6.2)]. Inform patients of the signs and symptoms of anaphylaxis, and instruct them to seek immediate medical care should signs or symptoms occur.

Once Omalizumab-igec therapy has been established, administration of Omalizumab-igec prefilled syringe outside of a healthcare setting by a patient or a caregiver may be appropriate for selected patients. Patient selection, determined by the healthcare provider in consultation with the patient, should take into account the pattern of anaphylaxis events seen in premarketing clinical trials and postmarketing spontaneous reports, as well as individual patient risk factors (e.g., prior history of anaphylaxis), ability to recognize signs and symptoms of anaphylaxis, and ability to perform subcutaneous injections with Omalizumab-igec prefilled syringe or autoinjector with proper technique according to the prescribed dosing regimen and Instructions for Use [see Dosage and Administration (2.6), Adverse Reactions (6.1, 6.2)].

Discontinue Omalizumab-igec in patients who experience a severe hypersensitivity reaction [see Contraindications (4)].

5.2 Malignancy

Malignant neoplasms were observed in 20 of 4,127 (0.5%) omalizumab-treated patients compared with 5 of 2,236 (0.2%) control patients in clinical studies of adults and adolescents ≥12 years of age with asthma and other allergic disorders. The observed malignancies in omalizumab-treated patients were a variety of types, with breast, non-melanoma skin, prostate, melanoma, and parotid occurring more than once, and five other types occurring once each. The majority of patients were observed for less than 1 year. The impact of longer exposure to omalizumab products or use in patients at higher risk for malignancy (e.g., elderly, current smokers) is not known.

In a subsequent observational study of 5,007 omalizumab-treated and 2,829 non-omalizumab- treated adolescent and adult patients with moderate to severe persistent asthma and a positive skin test reaction or in vitro reactivity to a perennial aeroallergen, patients were followed for up to 5 years. In this study, the incidence rates of primary malignancies (per 1,000 patient years) were similar among omalizumab-treated (12.3) and non-omalizumab-treated patients (13.0) [see Adverse Reactions (6.1)]. However, study limitations preclude definitively ruling out a malignancy risk with omalizumab products. Study limitations include: the observational study design, the bias introduced by allowing enrollment of patients previously exposed to omalizumab (88%), enrollment of patients (56%) while a history of cancer or a premalignant condition were study exclusion criteria, and the high study discontinuation rate (44%).

5.3 Acute Asthma Symptoms and Deteriorating Disease

Omalizumab products have not been shown to alleviate asthma exacerbations acutely. Do not use Omalizumab-igec to treat acute bronchospasm or status asthmaticus. Patients should seek medical advice if their asthma remains uncontrolled or worsens after initiation of treatment with Omalizumab-igec.

5.4 Corticosteroid Reduction

Do not discontinue systemic or inhaled corticosteroids abruptly upon initiation of Omalizumab-igec therapy for asthma or CRSwNP. Decrease corticosteroids gradually under the direct supervision of a physician. In CSU patients, the use of omalizumab products in combination with corticosteroids has not been evaluated.

5.5 Eosinophilic Conditions

In rare cases, patients with asthma on therapy with omalizumab products may present with serious systemic eosinophilia sometimes presenting with clinical features of vasculitis consistent with Churg-Strauss syndrome, a condition which is often treated with systemic corticosteroid therapy. These events usually, but not always, have been associated with the reduction of oral corticosteroid therapy. Physicians should be alert to eosinophilia, vasculitic rash, worsening pulmonary symptoms, cardiac complications, and/or neuropathy presenting in their patients. A causal association between omalizumab products and these underlying conditions has not been established.

5.6 Fever, Arthralgia, and Rash

In post-approval use, some patients have experienced a constellation of signs and symptoms including arthritis/arthralgia, rash, fever, and lymphadenopathy with an onset 1 to 5 days after the first or subsequent injections of omalizumab products. These signs and symptoms have recurred after additional doses in some patients. Although circulating immune complexes or a skin biopsy consistent with a Type III reaction were not seen with these cases, these signs and symptoms are similar to those seen in patients with serum sickness. Physicians should stop Omalizumab-igec if a patient develops this constellation of signs and symptoms [see Adverse Reactions (6.2)].

5.7 Parasitic (Helminth) Infection

Monitor patients at high risk of geohelminth infection while on Omalizumab-igec therapy. Insufficient data are available to determine the length of monitoring required for geohelminth infections after stopping omalizumab products treatment.

In a one-year clinical trial conducted in Brazil in adult and adolescent patients at high risk for geohelminthic infections (roundworm, hookworm, whipworm, threadworm), 53% (36/68) of omalizumab-treated patients experienced an infection, as diagnosed by standard stool examination, compared to 42% (29/69) of placebo controls. The point estimate of the odds ratio for infection was 1.96, with a 95% confidence interval (0.88, 4.36) indicating that in this study a patient who had an infection was anywhere from 0.88 to 4.36 times as likely to have received omalizumab than a patient who did not have an infection. Response to appropriate anti-geohelminth treatment of infection as measured by stool egg counts was not different between treatment groups.

5.8 Laboratory Tests

Serum total IgE levels increase following administration of omalizumab products due to formation of drug:IgE complexes [see Clinical Pharmacology (12.2)]. Elevated serum total IgE levels may persist for up to 1 year following discontinuation of omalizumab products. Do not use serum total IgE levels obtained less than 1 year following discontinuation to reassess the dosing regimen for asthma, CRSwNP or IgE-mediated food allergy patients, because these levels may not reflect steady- state free IgE levels [see Dosage and Administration (2.2, 2.3, 2.4)].

5.9 Potential Medication Error Related to Emergency Treatment of Anaphylaxis

Omalizumab-igec should not be used for the emergency treatment of allergic reactions, including anaphylaxis. In studies to simulate use, some patients and caregivers did not understand that omalizumab products are not intended for the emergency treatment of allergic reactions, including anaphylaxis. The safety and effectiveness of omalizumab products for emergency treatment of allergic reactions, including anaphylaxis, have not been established. Instruct patients that Omalizumab-igec is for maintenance use to reduce allergic reactions, including anaphylaxis, while avoiding food allergens.

6 ADVERSE REACTIONS

The following clinically significant adverse reactions are described elsewhere in the labeling:

- Anaphylaxis [see Boxed Warning and Warnings and Precautions (5.1)]
- Malignancies [see Warnings and Precautions (5.2)]

6.1 Clinical Trials Experience

Because clinical trials are conducted under widely varying conditions, adverse reaction rates observed in the clinical trials of a drug cannot be directly compared to rates in the clinical trials of another drug and may not reflect the rates observed in clinical practice.

Adverse Reactions from Clinical Studies in Adult and Adolescent Patients 12 Years of Age and Older with Asthma

The data described below reflect omalizumab exposure for 2,076 adult and adolescent patients ages 12 and older, including 1,687 patients exposed for six months and 555 exposed for one year or more, in either placebo-controlled or other controlled asthma studies. The mean age of patients receiving omalizumab was 42 years, with 134 patients 65 years of age or older; 60% were women, and 85% Caucasian. Patients received omalizumab 150 mg to 375 mg every 2 or 4 weeks or, for patients assigned to control groups, standard therapy with or without a placebo.

The adverse reactions most frequently resulting in clinical intervention (e.g., discontinuation of omalizumab, or the need for concomitant medication to treat an adverse reaction) were injection site reaction (45%), viral infections (23%), upper respiratory tract infection (20%), sinusitis (16%), headache (15%), and pharyngitis (11%). These reactions were observed at similar rates in omalizumab-treated patients and control patients.

Table 6 shows adverse reactions from four placebo-controlled asthma trials that occurred ≥1% and more frequently in adult and adolescent patients 12 years of age and older receiving omalizumab than in those receiving placebo. Adverse reactions were classified using preferred terms from the International Medical Nomenclature (IMN) dictionary. Injection site reactions were recorded separately from the reporting of other adverse reactions.

Table 6. Adverse Reactions ≥1% More Frequent in omalizumab-Treated Adult or Adolescent Patients 12 years of Age and Older in Four Placebo-controlled Asthma Trials
Adverse reaction | Omalizumab n=738 | Placebo n=717
Body as a whole
Pain | 7% | 5%
Fatigue | 3% | 2%
Musculoskeletal system
Arthralgia | 8% | 6%
Fracture | 2% | 1%
Leg pain | 4% | 2%
Arm pain | 2% | 1%
Nervous system
Dizziness | 3% | 2%
Skin and appendages
Pruritus | 2% | 1%
Dermatitis | 2% | 1%
Special senses
Earache | 2% | 1%

There were no differences in the incidence of adverse reactions based on age (among patients under 65), gender or race.

Anaphylaxis Case Control Study

A retrospective case-control study investigated risk factors for anaphylaxis to omalizumab among patients treated with omalizumab for asthma. Cases with an adjudicated history of anaphylaxis to omalizumab were compared to controls with no such history. The study found that a self-reported history of anaphylaxis to foods, medications or other causes was more common among patients with omalizumab anaphylaxis (57% of 30 cases) compared to controls (23% of 88 controls) [OR 8.1, 95% CI 2.7 to 24.3]. Because this is a case-control study, the study cannot provide the incidence of anaphylaxis among omalizumab users. From other sources, anaphylaxis to omalizumab was observed in 0.1% of patients in clinical trials and at least 0.2% of patients based upon postmarketing reports. Approximately 60% to 70% of cases were reported to occur within the first three doses of omalizumab, with additional cases occurring sporadically beyond the third dose. The time to onset for anaphylaxis was reported to occur within 2 hours for the majority of cases (approximately 75%) [see Warnings and Precautions (5.1), Adverse Reactions (6.2)].

Injection Site Reactions

In adults and adolescents, injection site reactions of any severity occurred at a rate of 45% in omalizumab-treated patients compared with 43% in placebo-treated patients. The types of injection site reactions included: bruising, redness, warmth, burning, stinging, itching, hive formation, pain, indurations, mass, and inflammation.

Severe injection site reactions occurred more frequently in omalizumab-treated patients compared with patients in the placebo group (12% versus 9%).

The majority of injection site reactions occurred within 1 hour post injection, lasted less than 8 days, and generally decreased in frequency at subsequent dosing visits.

Adverse Reactions from Clinical Studies in Pediatric Patients 6 to <12 Years of Age with Asthma

The data described below reflect omalizumab exposure for 926 patients 6 to <12 years of age, including 583 patients exposed for six months and 292 exposed for one year or more, in either placebo-controlled or other controlled asthma studies. The mean age of pediatric patients receiving omalizumab was 8.8 years; 69% were male, and 64% were Caucasian. Pediatric patients received omalizumab 75 mg to 375 mg every 2 or 4 weeks or, for patients assigned to control groups, standard therapy with or without a placebo. No cases of malignancy were reported in patients treated with omalizumab in these trials.

The most common adverse reactions occurring at ≥3% in the pediatric patients receiving omalizumab and more frequently than in patients treated with placebo were nasopharyngitis, headache, pyrexia, upper abdominal pain, pharyngitis streptococcal, otitis media, viral gastroenteritis, arthropod bite, and epistaxis.

The adverse reactions most frequently resulting in clinical intervention (e.g., discontinuation of omalizumab, or the need for concomitant medication to treat an adverse event) were bronchitis (0.2%), headache (0.2%) and urticaria (0.2%). These reactions were observed at similar rates in omalizumab-treated patients and control patients.

Adverse Reactions from Clinical Studies in Adult Patients with Chronic Rhinosinusitis with Nasal Polyps

The data described below reflect omalizumab exposure for 135 patients ≥ 18 years of age, exposed for six months in two placebo-controlled studies. The mean age of patients receiving omalizumab was 49.7 years; 64% were male, and 94% were Caucasian. Patients received omalizumab or placebo SC every 2 or 4 weeks, with dosage and frequency according to Table 3. All patients received background nasal mometasone therapy throughout the study. Table 7 lists the adverse reactions occurring in ≥3% of omalizumab-treated patients and more frequently than in patients treated with placebo in chronic rhinosinusitis with nasal polyps (CRSwNP) Trials 1 and 2; results were pooled.

Table 7. Adverse Reactions Occurring in ≥3% of omalizumab-Treated Patients and More Frequently than in Patients Treated with Placebo in CRSwNP Trials 1 and 2
Adverse reaction | Omalizumab N=135 | Placebo N=130
Gastrointestinal disorder
Upper abdominal pain | 4 (3.0%) | 1 (0.8%)
General disorders and administration site conditions
Injection site reactions [Injection site reactions terms: 'injection site reaction', 'injection related reaction' and 'injection site pain'. All injection site reactions were mild to moderate severity and none resulted in study discontinuation] | 7 (5.2%) | 2 (1.5%)
Musculoskeletal system and connective tissue disorders
Arthralgia | 4 (3.0%) | 2 (1.5%)
Nervous system disorders
Headache | 11 (8.1%) | 7 (5.4%)
Dizziness | 4 (3.0%) | 1 (0.8%)
CRSwNP = Chronic Rhinosinusitis with Nasal Polyps.

Adverse Reactions from a Clinical Study in Patients with IgE-Mediated Food Allergy

The safety of omalizumab in patients with IgE-mediated allergic reactions (Type I), including anaphylaxis, that may occur with accidental exposure to one or more foods, was based on data from the Food Allergy (FA) Trial, a randomized, double-blind, placebo-controlled trial in 168 patients (165 pediatric patients and 3 adults) who were allergic to peanut and at least two other foods [see Clinical Studies (14.3)]. Patients received a dosage of omalizumab or placebo subcutaneously every 2 or 4 weeks for 16 to 20 weeks according to the recommended dosage based on total IgE level (IU/mL), measured before the start of treatment, and by body weight (kg) provided in Table 4 [see Dosage and Administration (2.4)]. Safety data provided in Table 8 are from the primary analysis population of pediatric patients aged 1 years to 17 years. Safety data obtained from adults (n=3) in this trial was limited. Table 8 lists the adverse reactions occurring in ≥3% of omalizumab-treated pediatric patients and more frequently than in patients treated with placebo in the FA trial. There were no discontinuations due to adverse reactions.

Table 8. Adverse Reactions Occurring in ≥3% of omalizumab -Treated Pediatric Patients 1 Year of Age and Older and More Frequently than in Patients Treated with Placebo in FA Trial
Adverse reaction | Omalizumab N=110 | Placebo N=55
General disorders and administration site conditions
Injection site reactions [Injection site reactions terms: 'injection site reaction','injection site urticaria','injection site discomfort','injection site erythema','injection site pain' and 'injection site rash'. All injection site reactions were mild to moderate severity and none resulted in study discontinuation.] | 17 (15.5%) | 6 (10.9%)
Pyrexia | 7 (6.4%) | 2 (3.6%)

Adverse Reactions from Clinical Studies in Patients with Chronic Spontaneous Urticaria (CSU)

The safety of omalizumab for the treatment of chronic spontaneous urticaria (CSU) was assessed in three placebo-controlled, multiple-dose clinical trials of 12 weeks' (CSU Trial 2) and 24 weeks' duration (CSU Trials 1 and 3). In CSU Trials 1 and 2, patients received omalizumab 75 mg, 150 mg, or 300 mg or placebo every 4 weeks in addition to their baseline level of H1 antihistamine therapy throughout the treatment period. In CSU Trial 3 patients were randomized to omalizumab 300 mg or placebo every 4 weeks in addition to their baseline level of H1 antihistamine therapy. The data described below reflect omalizumab exposure for 733 patients enrolled and receiving at least one dose of omalizumab in the three clinical trials, including 684 patients exposed for 12 weeks and 427 exposed for 24 weeks. The mean age of patients receiving omalizumab 300 mg was 43 years, 75% were women, and 89% were white. The demographic profiles for patients receiving omalizumab 150 mg and 75 mg were similar.

Table 9 shows adverse reactions that occurred in ≥2% of patients receiving omalizumab (150 or 300 mg) and more frequently than those receiving placebo. Adverse reactions are pooled from CSU Trial 2 and the first 12 weeks of CSU Trials 1 and 3.

Table 9. Adverse Reactions Occurring in ≥2% in omalizumab-Treated Patients and More Frequently than in Patients Treated with Placebo (Day 1 to Week 12) in CSU Trials
Adverse Reactions [by MedDRA (15.1) System Organ Class and Preferred Term] | CSU Trials 1, 2 and 3 Pooled
Adverse Reactions [by MedDRA (15.1) System Organ Class and Preferred Term] | 150 mg (n=175) | 300 mg (n=412) | Placebo (n=242)
Gastrointestinal disorders
Nausea | 2 (1.1%) | 11 (2.7%) | 6 (2.5%)
Infections and infestations
Nasopharyngitis | 16 (9.1%) | 27 (6.6%) | 17 (7.0%)
Sinusitis | 2 (1.1%) | 20 (4.9%) | 5 (2.1%)
Upper respiratory tract infection | 2 (1.1%) | 14 (3.4%) | 5 (2.1%)
Viral upper respiratory tract infection | 4 (2.3%) | 2 (0.5%) | (0.0%)
Musculoskeletal and connective tissue disorders
Arthralgia | 5 (2.9%) | 12 (2.9%) | 1 (0.4%)
Nervous system disorders
Headache | 21 (12.0%) | 25 (6.1%) | 7 (2.9%)
Respiratory, thoracic, and mediastinal disorders
Cough | 2 (1.1%) | 9 (2.2%) | 3 (1.2%)

Additional reactions reported during the 24-week treatment period in CSU Trials 1 and 3 [≥2% of patients receiving omalizumab (150 mg or 300 mg) and more frequently than those receiving placebo] included: toothache, fungal infection, urinary tract infection, myalgia, pain in extremity, musculoskeletal pain, peripheral edema, pyrexia, migraine, sinus headache, anxiety, oropharyngeal pain, asthma, urticaria, and alopecia.

Injection Site Reactions in Patients with CSU

Injection site reactions of any severity occurred during the studies in more omalizumab-treated patients [11 patients (2.7%) at 300 mg, 1 patient (0.6%) at 150 mg] compared with 2 placebo-treated patients (0.8%). The types of injection site reactions included: swelling, erythema, pain, bruising, itching, bleeding, and urticaria. None of the events resulted in study discontinuation or treatment interruption.

Cardiovascular and Cerebrovascular Events from Clinical Studies in Patients with Asthma

A 5-year observational cohort study was conducted in patients ≥12 years of age with moderate to severe persistent asthma and a positive skin test reaction to a perennial aeroallergen to evaluate the long-term safety of omalizumab, including the risk of malignancy [see Warnings and Precautions (5.2)]. A total of 5,007 omalizumab-treated and 2,829 non– omalizumab-treated patients enrolled in the study. Similar percentages of patients in both cohorts were current (5%) or former smokers (29%). Patients had a mean age of 45 years and were followed for a mean of 3.7 years. More omalizumab-treated patients were diagnosed with severe asthma (50%) compared to the non–omalizumab-treated patients (23%) and 44% of patients prematurely discontinued the study. Additionally, 88% of patients in the omalizumab- treated cohort had been previously exposed to omalizumab for a mean of 8 months.

A higher incidence rate (per 1,000 patient-years) of overall cardiovascular and cerebrovascular serious adverse events (SAEs) was observed in omalizumab-treated patients (13.4) compared to non–omalizumab-treated patients (8.1). Increases in rates were observed for transient ischemic attack (0.7 versus 0.1), myocardial infarction (2.1 versus 0.8), pulmonary hypertension (0.5 versus 0), pulmonary embolism/venous thrombosis (3.2 versus 1.5), and unstable angina (2.2 versus 1.4), while the rates observed for ischemic stroke and cardiovascular death were similar among both study cohorts. The results suggest a potential increased risk of serious cardiovascular and cerebrovascular events in patients treated with omalizumab. However, the observational study design, the inclusion of patients previously exposed to omalizumab (88%), baseline imbalances in cardiovascular risk factors between the treatment groups, an inability to adjust for unmeasured risk factors, and the high study discontinuation rate limit the ability to quantify the magnitude of the risk.

A pooled analysis of 25 randomized double-blind, placebo-controlled clinical trials of 8 to 52 weeks in duration was conducted to further evaluate the imbalance in cardiovascular and cerebrovascular SAEs noted in the above observational cohort study. A total of 3,342 omalizumab-treated patients and 2,895 placebo-treated patients were included in the pooled analysis. The patients had a mean age of 38 years, and were followed for a mean duration of 6.8 months. No notable imbalances were observed in the rates of cardiovascular and cerebrovascular SAEs listed above. However, the results of the pooled analysis were based on a low number of events, slightly younger patients, and shorter duration of follow-up than the observational cohort study; therefore, the results are insufficient to confirm or reject the findings noted in the observational cohort study.

Adverse Reactions from Clinical Study in Healthy Adults

Injection Site Reactions in Healthy Adults

In an open label trial in healthy adults, in which the 300 mg/2 mL autoinjector was compared to the 300 mg/2 mL prefilled syringe, injection site reactions (e.g., induration, pain, erythema, hemorrhage, swelling, discomfort, bruising, hypoesthesia, edema, pruritus) were observed in 24% (16/66) of subjects treated with the autoinjector compared with 14% (9/64) of subjects treated with the prefilled syringe.

6.2 Postmarketing Experience

The following adverse reactions have been identified during postapproval use of omalizumab products. Because these reactions are reported voluntarily from a population of uncertain size, it is not always possible to reliably estimate their frequency or establish a causal relationship to drug exposure.

Anaphylaxis: Based on spontaneous reports and an estimated exposure of about 57,300 patients from June 2003 through December 2006, the frequency of anaphylaxis attributed to omalizumab use was estimated to be at least 0.2% of patients. Diagnostic criteria of anaphylaxis were skin or mucosal tissue involvement, and, either airway compromise, and/or reduced blood pressure with or without associated symptoms, and a temporal relationship to omalizumab administration with no other identifiable cause. Signs and symptoms in these reported cases included bronchospasm, hypotension, syncope, urticaria, angioedema of the throat or tongue, dyspnea, cough, chest tightness, and/or cutaneous angioedema. Pulmonary involvement was reported in 89% of the cases. Hypotension or syncope was reported in 14% of cases. Fifteen percent of the reported cases resulted in hospitalization. A previous history of anaphylaxis unrelated to omalizumab was reported in 24% of the cases.

Of the reported cases of anaphylaxis attributed to omalizumab, 39% occurred with the first dose, 19% occurred with the second dose, 10% occurred with the third dose, and the rest after subsequent doses. One case occurred after 39 doses (after 19 months of continuous therapy, anaphylaxis occurred when treatment was restarted following a 3-month gap). The time to onset of anaphylaxis in these cases was up to 30 minutes in 35%, greater than 30 and up to 60 minutes in 16%, greater than 60 and up to 90 minutes in 2%, greater than 90 and up to 120 minutes in 6%, greater than 2 hours and up to 6 hours in 5%, greater than 6 hours and up to 12 hours in 14%, greater than 12 hours and up to 24 hours in 8%, and greater than 24 hours and up to 4 days in 5%. In 9% of cases the times to onset were unknown.

Twenty-three patients who experienced anaphylaxis were rechallenged with omalizumab and 18 patients had a recurrence of similar symptoms of anaphylaxis. In addition, anaphylaxis occurred upon rechallenge with omalizumab in 4 patients who previously experienced urticaria only.

Eosinophilic Conditions: Eosinophilic conditions have been reported [see Warnings and Precautions (5.5)].

Fever, Arthralgia, and Rash: A constellation of signs and symptoms including arthritis/arthralgia, rash (urticaria or other forms), fever and lymphadenopathy similar to serum sickness have been reported in post-approval use of omalizumab products [see Warnings and Precautions (5.6)].

Hematologic: Severe thrombocytopenia has been reported.

Skin: Hair loss has been reported.

7 DRUG INTERACTIONS

No formal drug interaction studies have been performed with omalizumab products.

In patients with asthma, CRSwNP, and IgE-mediated food allergy the concomitant use of omalizumab products and allergen immunotherapy has not been evaluated.

In patients with CSU, the use of omalizumab products in combination with immunosuppressive therapies has not been studied.

8 USE IN SPECIFIC POPULATIONS

8.1 Pregnancy

Risk Summary

A registry study of omalizumab exposure during pregnancy showed no increase in the rate of major birth defects or miscarriage. There was an increased rate of low birth weight among registry infants compared to infants in the other cohorts, despite average gestational age at birth; however, women taking omalizumab during pregnancy also had more severe asthma, which makes it difficult to determine whether the low birth weight is due to the drug or the disease severity [see Data]. There are risks associated with poorly or moderately controlled asthma in pregnancy [see Clinical Considerations].

Human IgG antibodies are known to cross the placental barrier; therefore, omalizumab products may be transmitted from the mother to the developing fetus.

In animal reproduction studies, no evidence of fetal harm was observed in Cynomolgus monkeys with subcutaneous doses of omalizumab up to approximately 5 times the maximum recommended human dose (MRHD) [see Data].

The estimated background risk of major birth defects and miscarriage for the indicated population(s) is unknown. All pregnancies have a background risk of birth defect, loss, or other adverse outcomes. In the US general population, the estimated background risk of major birth defects and miscarriage in clinically recognized pregnancies is 2% to 4% and 15% to 20%, respectively.

Clinical Considerations

Disease-associated maternal and/or embryo/fetal risk

In women with poorly or moderately controlled asthma, evidence demonstrates that there is an increased risk of preeclampsia in the mother and prematurity, low birth weight, and small for gestational age in the neonate. The level of asthma control should be closely monitored in pregnant women and treatment adjusted as necessary to maintain optimal control.

Data

Human Data

A prospective cohort pregnancy exposure registry study conducted in the US from 2006 to 2018, included 250 pregnant women with asthma treated with omalizumab. Of these, 246 patients were exposed to omalizumab in the first trimester of pregnancy, and the median exposure duration was 8.7 months.

The registry findings for applicable mother and infant subgroups were compared to age- adjusted frequencies in a disease-matched external cohort of 1,153 pregnant women with asthma (without exposure to omalizumab) identified from healthcare databases of residents in the Canadian province of Quebec, and referred to as the Quebec External Comparator Cohort ("comparator cohort").

Among applicable registry infants, the prevalence of major congenital anomalies (8.1%) was similar to that for infants in the comparator cohort (8.9%). Among applicable registry pregnancies, 99.1% led to live births, similar to 99.3% for the comparator cohort. There was an increased rate of low birth weight among registry infants (13.7%) as compared to the comparator cohort (9.8%); however, women taking omalizumab during pregnancy also had more severe asthma, which makes it difficult to determine whether the low birth weight is due to the drug or the disease severity.

The registry study cannot definitively establish the absence of any risk because of methodological limitations, including the observational nature of the registry, small sample size, and potential differences between the registry population and the comparator cohort.

Animal Data

Reproductive studies have been performed in Cynomolgus monkeys. There was no evidence of maternal toxicity, embryotoxicity, or teratogenicity when omalizumab was administered throughout the period of organogenesis at doses that produced exposures approximately 5 times the MRHD (on a mg/kg basis with maternal subcutaneous doses up to 75 mg/kg/week). Omalizumab did not elicit adverse effects on fetal or neonatal growth when administered throughout late gestation, delivery, and nursing.

8.2 Lactation

Risk Summary

There is no information regarding the presence of omalizumab products in human milk, or the effects on milk production. However, omalizumab products are human monoclonal antibodies (IgG1 kappa), and immunoglobulin (IgG) is present in human milk in small amounts.

The majority of infants (80.9%, 186/230) in the pregnancy exposure registry were breastfed. Events categorized as "infections and infestations" were not significantly increased in infants who were exposed to omalizumab through breastfeeding compared with infants who were not breastfed, or infants who were breastfed without exposure to omalizumab.

The developmental and health benefits of breastfeeding should be considered along with the mother's clinical need for Omalizumab-igec and any potential adverse effects on the breastfed child from Omalizumab-igec or from the underlying maternal condition.

8.4 Pediatric Use

Asthma

Safety and effectiveness of Omalizumab-igec for moderate to severe persistent asthma who had a positive skin test or in vitro reactivity to a perennial aeroallergen and whose symptoms are inadequately controlled with inhaled corticosteroids, have been established in pediatric patients aged 6 years and older. Use of Omalizumab-igec for this indication is supported by evidence from adequate and well-controlled studies of omalizumab. Omalizumab was evaluated in 2 trials in 926 (omalizumab 624; placebo 302) pediatric patients 6 to <12 years of age with moderate to severe persistent asthma who had a positive skin test or in vitro reactivity to a perennial aeroallergen. One trial was a pivotal trial of similar design and conduct to that of adult and adolescent Asthma Trials 1 and 2. The other trial was primarily a safety study and included evaluation of efficacy as a secondary outcome. In the pivotal trial, omalizumab-treated patients had a statistically significant reduction in the rate of exacerbations (exacerbation was defined as worsening of asthma that required treatment with systemic corticosteroids or a doubling of the baseline ICS dose) [see Clinical Studies (14.1)].

Safety and efficacy of Omalizumab-igec in pediatric patients with asthma below 6 years of age have not been established.

Chronic Rhinosinusitis with Nasal Polyps

Safety and effectiveness of Omalizumab-igec in pediatric patients with chronic rhinosinusitis with nasal polyps (CRSwNP) below 18 years of age have not been established.

IgE-Mediated Food Allergy

The safety and effectiveness of Omalizumab-igec for the reduction of allergic reactions (Type I), including anaphylaxis, that may occur with accidental exposure to one or more foods have been established in pediatric patients aged 1 year and older with IgE-mediated food allergy. Use of Omalizumab-igec for this indication is supported by evidence from an adequate and well-controlled study that included a total of 165 pediatric patients; 61 patients aged 1 year to less than 6 years of age and 104 patients aged 6 to less than 18 years of age. A significantly greater percentage of omalizumab-treated patients compared to placebo-treated patients was able to consume a single dose of food (peanut, cashew, milk, egg) without dose-limiting symptoms [see Clinical Studies (14.3)].

Safety and effectiveness in pediatric patients with IgE-mediated food allergy below 1 year of age have not been established.

Chronic Spontaneous Urticaria

The safety and effectiveness of Omalizumab-igec for chronic spontaneous urticaria (CSU) who remain symptomatic despite H1 antihistamine treatment have been established in pediatric patients aged 12 years and older. Use of Omalizumab-igec in this population is supported by evidence from adequate and well-controlled studies of omalizumab. Adolescent patients with CSU were evaluated in 39 patients 12 to 17 years of age (omalizumab 29, placebo 10) included in three randomized, placebo-controlled CSU trials. A numerical decrease in weekly itch score was observed, and adverse reactions were similar to those reported in patients 18 years and older.

Safety and effectiveness of Omalizumab-igec in pediatric patients with CSU below 12 years of age have not been established.

8.5 Geriatric Use

In clinical studies, 134 asthma patients, 20 CRSwNP patients, 37 CSU patients and no IgE-mediated food allergy patients 65 years of age or older were treated with omalizumab. Although there were no apparent age-related differences observed in these studies, the number of patients aged 65 and over is not sufficient to determine whether they respond differently from younger patients.

11 DESCRIPTION

Omalizumab-igec is a recombinant DNA-derived humanized IgG1κ monoclonal antibody that selectively binds to human immunoglobulin E (IgE). The antibody has a molecular weight of approximately 149 kiloDaltons. Omalizumab-igec is produced by a Chinese hamster ovary cell suspension culture.

Omalizumab-igec is administered as a subcutaneous (SC) injection and is available in prefilled syringes.

Omalizumab-igec Injection (Prefilled Syringe)

Omalizumab-igec injection is supplied as a sterile, preservative-free, clear to opalescent and colorless to pale brownish-yellow solution for subcutaneous injection.

Omalizumab-igec injection is available as a single-dose prefilled syringe.

Each 75 mg prefilled syringe delivers 75 mg omalizumab-igec in 0.5 mL and contains arginine hydrochloride (21.065 mg), histidine (0.685 mg), L-histidine hydrochloride monohydrate (1.17 mg), and polysorbate 20 (0.2 mg) in Water for Injection (WFI), USP. The pH of the product is 6.0.

Each 150 mg prefilled syringe delivers 150 mg omalizumab-igec in 1 mL and contains arginine hydrochloride (42.13 mg), histidine (1.37 mg), L-histidine hydrochloride monohydrate (2.34 mg), and polysorbate 20 (0.4 mg) in WFI, USP. The pH of the product is 6.0.

Each 300 mg prefilled syringe delivers 300 mg omalizumab-igec in 2 mL and contains arginine hydrochloride (84.26 mg), histidine (2.74 mg), L-histidine hydrochloride monohydrate (4.68 mg), and polysorbate 20 (0.8 mg) in WFI, USP. The pH of the product is 6.0.

12 CLINICAL PHARMACOLOGY

12.1 Mechanism of Action

Asthma, Chronic Rhinosinusitis with Nasal Polyps, and IgE-Mediated Food Allergy

Omalizumab products inhibit the binding of IgE to the high-affinity IgE receptor (FcεRI) on the surface of mast cells, basophils, and dendritic cells, resulting in FcεRI down-regulation on these cells.

In allergic asthmatics, treatment with omalizumab products inhibit IgE-mediated inflammation, as evidenced by reduced blood and tissue eosinophils and reduced inflammatory mediators, including IL-4, IL-5, and IL-13.

Chronic Spontaneous Urticaria

Omalizumab products bind to IgE and lowers free IgE levels. Subsequently, IgE receptors (FcεRI) on cells down-regulate. The mechanism by which these effects of omalizumab products result in an improvement of chronic spontaneous urticaria (CSU) symptoms is unknown.

12.2 Pharmacodynamics

Asthma

In clinical studies, serum free IgE levels were reduced in a dose-dependent manner within 1 hour following the first dose and maintained between doses. Mean serum free IgE decrease was greater than 96% using recommended doses. Serum total IgE levels (i.e., bound and unbound) increased after the first dose due to the formation of drug:IgE complexes, which have a slower elimination rate compared with free IgE. At 16 weeks after the first dose, average serum total IgE levels were five-fold higher compared with pre-treatment when using standard assays. After discontinuation of omalizumab dosing, the omalizumab -induced increase in total IgE and decrease in free IgE were reversible, with no observed rebound in IgE levels after drug washout. Total IgE levels did not return to pre-treatment levels for up to one year after discontinuation of omalizumab.

Chronic Rhinosinusitis with Nasal Polyps

In clinical studies in chronic rhinosinusitis with nasal polyps (CRSwNP) patients, omalizumab treatment led to a reduction in serum free IgE and an increase in serum total IgE levels, similar to the observations in asthma patients. The mean total IgE concentrations at baseline were 168 IU/mL and 218 IU/mL in CRSwNP Trial 1 and 2, respectively. After repeated dosing every 2 or 4 weeks, with dosage and frequency according to Table 3, the mean predose free IgE concentrations at Week 16 were 10.0 IU/mL in CRSwNP Trial 1 and 11.7 IU/mL in CRSwNP Trial 2 and remained stable at 24 weeks of treatment. Total IgE levels in serum increased due to the formation of omalizumab-IgE complexes, which have a slower elimination rate compared with free IgE. After repeated dosing every 2 or 4 weeks, with dosage and frequency according to Table 3, mean and median predose serum total IgE levels at Week 16 were 3- to 4- fold higher compared with pre-treatment levels, and remained stable between 16 and 24 weeks of treatment.

IgE-Mediated Food Allergy

In a clinical study in patients with IgE-mediated food allergy, omalizumab treatment led to a reduction in serum free IgE and an increase in serum total IgE levels, similar to the observations in asthma patients. The mean total IgE concentration at baseline was 810 IU/mL. After repeated dosing every 2 or 4 weeks, with dosage and frequency according to Table 4, the mean pre-dose free IgE concentration at Week 16 was 10.0 IU/mL. Mean total IgE levels in serum increased about 2.4-fold due to the formation of omalizumab-IgE complexes, which have a longer half-life compared with free IgE.

Chronic Spontaneous Urticaria

In clinical studies in chronic spontaneous urticaria (CSU) patients, omalizumab treatment led to a dose-dependent reduction of serum free IgE and an increase of serum total IgE levels, similar to the observations in asthma patients. Maximum suppression of free IgE was observed 3 days following the first subcutaneous dose. After repeat dosing once every 4 weeks, predose serum free IgE levels remained stable between 12 and 24 weeks of treatment. Total IgE levels in serum increased after the first dose due to the formation of omalizumab-IgE complexes which have a slower elimination rate compared with free IgE. After repeat dosing once every 4 weeks at 75 mg up to 300 mg, average predose serum total IgE levels at Week 12 were two- to three-fold higher compared with pre-treatment levels, and remained stable between 12 and 24 weeks of treatment. After discontinuation of omalizumab dosing, free IgE levels increased and total IgE levels decreased towards pre-treatment levels over a 16-week follow-up period.

12.3 Pharmacokinetics

After SC administration, omalizumab was absorbed with an average absolute bioavailability of 62%. Following a single SC dose in adult and adolescent patients with asthma, omalizumab was absorbed slowly, reaching peak serum concentrations after an average of 7– 8 days. In patients with CSU, the peak serum concentration was reached at a similar time after a single SC dose. The pharmacokinetics of omalizumab was linear at doses greater than 0.5 mg/kg. In patients with asthma, following multiple doses of omalizumab, areas under the serum concentration-time curve from Day 0 to Day 14 at steady state were up to 6-fold of those after the first dose. In patients with CSU, omalizumab exhibited linear pharmacokinetics across the dose range of 75 mg to 600 mg given as single subcutaneous dose. Following repeat dosing from 75 to 300 mg every 4 weeks, trough serum concentrations of omalizumab increased proportionally with the dose levels.

In vitro, omalizumab formed complexes of limited size with IgE. Precipitating complexes and complexes larger than 1 million daltons in molecular weight were not observed in vitro or in vivo. Tissue distribution studies in Cynomolgus monkeys showed no specific uptake of ^125I-omalizumab by any organ or tissue. The apparent volume of distribution of omalizumab in patients with asthma following SC administration was 78 ± 32 mL/kg. In patients with CSU, based on population pharmacokinetics, distribution of omalizumab was similar to that in patients with asthma.

Clearance of omalizumab involved IgG clearance processes as well as clearance via specific binding and complex formation with its target ligand, IgE. Liver elimination of IgG included degradation in the liver reticuloendothelial system (RES) and endothelial cells. Intact IgG was also excreted in bile. In studies with mice and monkeys, drug:IgE complexes were eliminated by interactions with Fcɣ receptors within the RES at rates that were generally faster than IgG clearance. In asthma patients omalizumab serum elimination half-life averaged 26 days, with apparent clearance averaging 2.4 ± 1.1 mL/kg/day.

Doubling body weight approximately doubled apparent clearance. In CSU patients, at steady state, based on population pharmacokinetics, omalizumab serum elimination half-life averaged 24 days and apparent clearance averaged 240 mL/day (corresponding to 3.0 mL/kg/day for an 80 kg patient).

Specific Populations

Asthma

The population pharmacokinetics of omalizumab was analyzed to evaluate the effects of demographic characteristics in patients with asthma. Analyses of these data suggested that no dose adjustments are necessary for age (6 to 76 years), race, ethnicity, or gender.

Chronic Rhinosinusitis with Nasal Polyps

The population pharmacokinetics analyses of omalizumab suggested that the pharmacokinetics of omalizumab in chronic rhinosinusitis with nasal polyps (CRSwNP) were consistent with that in asthma. Graphical covariate analyses were performed to evaluate the effects of demographic characteristics and other factors on omalizumab exposure and clinical responses. These analyses demonstrate that no dose adjustments are necessary for age (18 to 75 years) or gender. Race and ethnicity data are too limited in CRSwNP studies to inform dose adjustment.

IgE-Mediated Food Allergy

Population pharmacokinetic (PK) analyses of omalizumab suggested that the PK of omalizumab in patients with IgE-mediated food allergy were generally consistent with that in patients with asthma. Covariate analyses were performed to evaluate the effects of demographic characteristics and other factors on omalizumab exposure and clinical responses. These analyses demonstrate that no dose adjustments are necessary for age (1 year and older), race, ethnicity, or gender.

Chronic Spontaneous Urticaria

The population pharmacokinetics of omalizumab was analyzed to evaluate the effects of demographic characteristics and other factors on omalizumab exposure in patients with chronic spontaneous urticaria (CSU). Covariate effects were evaluated by analyzing the relationship between omalizumab concentrations and clinical responses. These analyses demonstrate that no dose adjustments are necessary for age (12 to 75 years), race/ethnicity, gender, body weight, body mass index, or baseline IgE level.

12.6 Immunogenicity

The observed incidence of anti-drug antibodies is highly dependent on the sensitivity and specificity of the assay. Differences in assay methods preclude meaningful comparisons of the incidence of anti-drug antibodies in the studies described below with the incidence of anti-drug antibodies in other studies, including those of omalizumab or of other omalizumab products.

Antibodies to omalizumab were detected in approximately 1/1723 (<0.1%) of patients treated with omalizumab in the clinical studies evaluated for asthma in patients 12 years of age and older. In three pediatric studies, antibodies to omalizumab were detected in one patient out of 581 patients 6 to <12 years of age treated with omalizumab and evaluated for antibodies. There were no detectable antibodies in the patients treated in the CSU clinical trials, but due to levels of omalizumab at the time of anti-therapeutic antibody sampling and missing samples for some patients, antibodies to omalizumab could only have been determined in 88% of the 733 patients treated in these clinical studies. The data reflect the percentage of patients whose test results were considered positive for antibodies to omalizumab in ELISA assays and are highly dependent on the sensitivity and specificity of the assays.

Anti-drug antibodies were not measured in the CRSwNP or IgE-mediated food allergy trials.

13 NONCLINICAL TOXICOLOGY

13.1 Carcinogenesis, Mutagenesis, Impairment of Fertility

No long-term studies have been performed in animals to evaluate the carcinogenic potential of omalizumab products.

There were no effects on fertility and reproductive performance in male and female Cynomolgus monkeys that received omalizumab at subcutaneous doses up to 75 mg/kg/week (approximately 5 times the maximum recommended human dose on a mg/kg basis).

14 CLINICAL STUDIES

14.1 Asthma

Adult and Adolescent Patients 12 Years of Age and Older

The safety and efficacy of omalizumab were evaluated in three randomized, double-blind, placebo-controlled, multicenter trials.

The trials enrolled patients 12 to 76 years old, with moderate to severe persistent (NHLBI criteria) asthma for at least one year, and a positive skin test reaction to a perennial aeroallergen. In all trials, omalizumab dosing was based on body weight and baseline serum total IgE concentration.

All patients were required to have a baseline IgE between 30 and 700 IU/mL and body weight not more than 150 kg. Patients were treated according to a dosing table to administer at least 0.016 mg/kg/IU (IgE/mL) of omalizumab or a matching volume of placebo over each 4-week period. The maximum omalizumab dose per 4 weeks was 750 mg.

In all three trials an exacerbation was defined as a worsening of asthma that required treatment with systemic corticosteroids or a doubling of the baseline ICS dose. Most exacerbations were managed in the outpatient setting and the majority were treated with systemic steroids. Hospitalization rates were not significantly different between omalizumab and placebo-treated patients; however, the overall hospitalization rate was small. Among those patients who experienced an exacerbation, the distribution of exacerbation severity was similar between treatment groups.

Asthma Trials 1 and 2

At screening, patients in Asthma Trials 1 and 2 had a forced expiratory volume in one second (FEV1) between 40% and 80% predicted. All patients had a FEV1 improvement of at least 12% following beta2-agonist administration. All patients were symptomatic and were being treated with inhaled corticosteroids (ICS) and short-acting beta2-agonists. Patients receiving other concomitant controller medications were excluded, and initiation of additional controller medications while on study was prohibited. Patients currently smoking were excluded.

Each trial was comprised of a run-in period to achieve a stable conversion to a common ICS (beclomethasone dipropionate), followed by randomization to omalizumab or placebo. Patients received omalizumab for 16 weeks with an unchanged corticosteroid dose unless an acute exacerbation necessitated an increase. Patients then entered an ICS reduction phase of 12 weeks during which ICS dose reduction was attempted in a step-wise manner.

The distribution of the number of asthma exacerbations per patient in each group during a study was analyzed separately for the stable steroid and steroid-reduction periods.

In both Asthma Trials 1 and 2 the number of exacerbations per patient was reduced in patients treated with omalizumab compared with placebo (Table 10).

Measures of airflow (FEV1) and asthma symptoms were also evaluated in these trials. The clinical relevance of the treatment-associated differences is unknown. Results from the stable steroid phase Asthma Trial 1 are shown in Table 11. Results from the stable steroid phase of Asthma Trial 2 and the steroid reduction phases of both Asthma Trials 1 and 2 were similar to those presented in Table 11.

Table 10. Frequency of Asthma Exacerbations per Patient by Phase in Asthma Trials 1 and 2
 | Stable Steroid Phase (16 wks)
 | Asthma Trial 1 |  | Asthma Trial 2
Exacerbations per patient | omalizumab N=268 | Placebo N=257 | omalizumab N=274 | Placebo N=272
0 | 85.8% | 76.7% | 87.6% | 69.9%
1 | 11.9% | 16.7% | 11.3% | 25.0%
≥2 | 2.2% | 6.6% | 1.1% | 5.1%
p-Value | 0.005 |  | <0.001
Mean number exacerbations/patient | 0.2 | 0.3 | 0.1 | 0.4
 | Steroid Reduction Phase (12 wks)
Exacerbations per patient | omalizumab N=268 | Placebo N=257 | omalizumab N=274 | Placebo N=272
0 | 78.7% | 67.7% | 83.9% | 70.2%
1 | 19.0% | 28.4% | 14.2% | 26.1%
≥2 | 2.2% | 3.9% | 1.8% | 3.7%
p-Value | 0.004 |  | <0.001
Mean number exacerbations/patient | 0.2 | 0.4 | 0.2 | 0.3

Table 11. Asthma Symptoms and Pulmonary Function During Stable Steroid Phase of Asthma Trial 1
 | omalizumab N=268 [Number of patients available for analysis ranges 255-258 in the omalizumab group and 238-239 in the placebo group.] |  | Placebo N=257
Endpoint | Mean Baseline | Median Change (Baseline to Wk 16) | Mean Baseline | Median Change (Baseline to Wk 16)
Total asthma symptom score | 4.3 | –1.5 [Comparison of omalizumab versus placebo (p < 0.05).] | 4.2 | –1.1
Nocturnal asthma score | 1.2 | –0.4 | 1.1 | –0.2
Daytime asthma score | 2.3 | –0.9 | 2.3 | –0.6
FEV1 % predicted | 68 | 3 | 68 | 0
Asthma symptom scale: total score from 0 (least) to 9 (most); nocturnal and daytime scores from 0 (least) to 4 (most symptoms).

Asthma Trial 3

In Asthma Trial 3, there was no restriction on screening FEV1, and unlike Asthma Trials 1 and 2, long-acting beta2-agonists were allowed. Patients were receiving at least 1000 μg/day fluticasone propionate and a subset was also receiving oral corticosteroids. Patients receiving other concomitant controller medications were excluded, and initiation of additional controller medications while on study was prohibited. Patients currently smoking were excluded.

The trial was comprised of a run-in period to achieve a stable conversion to a common ICS (fluticasone propionate), followed by randomization to omalizumab or placebo. Patients were stratified by use of ICS-only or ICS with concomitant use of oral steroids. Patients received omalizumab for 16 weeks with an unchanged corticosteroid dose unless an acute exacerbation necessitated an increase. Patients then entered an ICS reduction phase of 16 weeks during which ICS or oral steroid dose reduction was attempted in a step-wise manner.

The number of exacerbations in patients treated with omalizumab was similar to that in placebo-treated patients (Table 12). The absence of an observed treatment effect may be related to differences in the patient population compared with Asthma Trials 1 and 2, study sample size, or other factors.

Table 12. Percentage of Patients with Asthma Exacerbations by Subgroup and Phase in Asthma Trial 3
 | Stable Steroid Phase (16 wks)
 | Inhaled Only |  | Oral + Inhaled
 | omalizumab N=126 | Placebo N=120 | omalizumab N=50 | Placebo N=45
% Patients with ≥1 exacerbations | 15.9% | 15.0% | 32.0% | 22.2%
Difference (95% CI) | 0.09 (–9.7, 13.7) |  | 9.8 (–10.5, 31.4)
 | Steroid Reduction Phase (16 wks)
 | omalizumab N=126 | Placebo N=120 | omalizumab N=50 | Placebo N=45
% Patients with ≥1 exacerbations | 22.2% | 26.7% | 42.0% | 42.2%
Difference (95% CI) | –4.4 (–17.6, 7.4) |  | –0. 2 (–22.4, 20.1)

In all three of the trials, a reduction of asthma exacerbations was not observed in the omalizumab-treated patients who had FEV1>80% at the time of randomization. Reductions in exacerbations were not seen in patients who required oral steroids as maintenance therapy.

Pediatric Patients 6 to <12 Years of Age

The safety and efficacy of omalizumab in pediatric patients 6 to <12 years of age with moderate to severe asthma is based on one randomized, double-blind, placebo controlled, multi-center trial (Asthma Trial 4 [NCT00079937]) and an additional supportive study (Asthma Trial 5).

Asthma Trial 4 was a 52-week study that evaluated the safety and efficacy of omalizumab as add-on therapy in 628 pediatric patients ages 6 to <12 years with moderate to severe asthma inadequately controlled despite the use of inhaled corticosteroids (fluticasone propionate DPI ≥200 mcg/day or equivalent) with or without other controller asthma medications. Eligible patients were those with a diagnosis of asthma >1 year, a positive skin prick test to at least one perennial aeroallergen, and a history of clinical features such as daytime and/or night-time symptoms and exacerbations within the year prior to study entry. During the first 24 weeks of treatment, steroid doses remained constant from baseline. This was followed by a 28-week period during which inhaled corticosteroid adjustment was allowed.

The primary efficacy variable was the rate of asthma exacerbations during the 24-week, fixed steroid treatment phase. An asthma exacerbation was defined as a worsening of asthma symptoms as judged clinically by the investigator, requiring doubling of the baseline inhaled corticosteroid dose for at least 3 days and/or treatment with rescue systemic (oral or IV) corticosteroids for at least 3 days. At 24 weeks, the omalizumab group had a statistically significantly lower rate of asthma exacerbations (0.45 vs. 0.64) with an estimated rate ratio of 0.69 (95% CI: 0.53, 0.90).

The omalizumab group also had a lower rate of asthma exacerbations compared to placebo over the full 52-week double-blind treatment period (0.78 vs. 1.36; rate ratio: 0.57; 95% CI: 0.45, 0.72). Other efficacy variables such as nocturnal symptom scores, beta-agonist use, and measures of airflow (FEV1) were not significantly different in omalizumab-treated patients compared to placebo.

Asthma Trial 5 was a 28-week randomized, double blind, placebo-controlled study that primarily evaluated safety in 334 pediatric patients, 298 of whom were 6 to <12 years of age, with moderate to severe asthma who were well-controlled with inhaled corticosteroids (beclomethasone dipropionate 168-420 mcg/day). A 16-week steroid treatment period was followed by a 12-week steroid dose reduction period. Patients treated with omalizumab had fewer asthma exacerbations compared to placebo during both the 16-week fixed steroid treatment period (0.18 vs. 0.32; rate ratio: 0.58; 95% CI: 0.35, 0.96) and the 28-week treatment period (0.38 vs. 0.76; rate ratio: 0.50; 95% CI: 0.36, 0.71).

14.2 Chronic Rhinosinusitis with Nasal Polyps

Adult Patients 18 Years of Age and Older

The safety and efficacy of omalizumab was evaluated in two, randomized, multicenter, double- blind, placebo-controlled clinical trials (CRSwNP Trial 1 [NCT03280550] and CRSwNP Trial 2 [NCT03280537]) that enrolled patients with chronic rhinosinusitis with nasal polyps (CRSwNP) with inadequate response to nasal corticosteroids (CRSwNP Trial 1, n=138; CRSwNP Trial 2, n=127).] and CRSwNP Trial 2 [NCT03280537]) that enrolled patients with chronic rhinosinusitis with nasal polyps (CRSwNP) with inadequate response to nasal corticosteroids (CRSwNP Trial 1, n=138; CRSwNP Trial 2, n=127).

Patients received omalizumab or placebo SC every 2 or 4 weeks, with omalizumab dosage and frequency according to Table 3, for 24 weeks followed by a 4-week follow-up period. All patients received background nasal mometasone therapy during both the treatment period and during a 5-week run-in period. Prior to randomization, patients were required to have evidence of bilateral polyps as determined by a nasal polyp score (NPS) ≥ 5 with NPS ≥ 2 in each nostril, despite use of nasal mometasone during the run-in period. NPS was measured via endoscopy and scored (range 0-4 per nostril: 0= no polyps; 1=small polyps in the middle meatus not reaching below the inferior border of the middle turbinate; 2=polyps reaching below the lower border of the middle turbinate; 3=large polyps reaching the lower border of the inferior turbinate or polyps medial to the middle turbinate; 4=large polyps causing complete obstruction of the inferior nasal cavity) for a total NPS (range 0-8). Patients were furthermore required to have a weekly average of nasal congestion score (NCS) > 1 prior to randomization, despite use of nasal mometasone. Nasal congestion was measured by a daily assessment on a 0 to 3 point severity scale (0=none, 1=mild, 2=moderate, 3=severe). Prior sino-nasal surgery or prior systemic corticosteroid usage were not required for inclusion in the trials and sinus CT scans were not performed to evaluate for sinus opacification.

Demographics and baseline characteristics, including allergic comorbidities, are described in Table 13.

Table 13. Demographics and Baseline Characteristics of CRSwNP Trials 1 and 2
Parameter | CRSwNP Trial 1 (n=138) | CRSwNP Trial 2 (n=127)
Mean age (years) (SD) | 51 (13) | 50 (12)
% Male | 64 | 65
Patients with systemic corticosteroid use in the previous year (%) | 19 | 26
Patients with prior surgery for nasal polyps (%) | 79 (57) | 79 (62)
Mean bilateral endoscopic NPS (SD), range 0-8 | 6.2 (1.0) | 6.3 (0.9)
Mean nasal congestion score (SD) range 0-3 | 2.4 (0.6) | 2.3 (0.7)
Mean sense of smell score (SD) range 0-3 | 2.7 (0.7) | 2.7 (0.7)
Mean post nasal drip score (SD) range 0-3 | 1.8 (0.9) | 1.7 (0.9)
Mean runny nose score (SD) range 0-3 | 2.0 (0.8) | 1.9 (0.9)
Mean blood eosinophils (cells/mcL) (SD) | 346 (284) | 335 (188)
Mean total IgE IU/mL (SD) | 161 (140) | 190 (201)
Asthma (%) | 54 | 61
Aspirin exacerbated respiratory disease (%) | 20 | 35
CRSwNP= chronic rhinosinusitis with nasal polyps; SD=standard deviation; NPS=nasal polyp score; IgE = Immunoglobulin E; IU=international units. For NPS, NCS, sense of smell, post nasal drip, and runny nose, higher scores indicate greater disease severity.

The co-primary endpoints in CRSwNP Trials 1 and 2 were NPS and average daily NCS at Week 24. In both trials, patients who received omalizumab had a statistically significant greater improvement from baseline at Week 24 in NPS and weekly average NCS, than patients who received placebo. Results from CRSwNP Trials 1 and 2 are shown in Table 14.

The greater improvements in NPS and NCS in the omalizumab group compared to the placebo group were observed as early as the first assessment at Week 4 in both studies, as seen in Figure 1.

Table 14. Change from Baseline at Week 24 in Nasal Polyp Score and 7-day Average of Daily Nasal Congestion Score in CRSwNP Trials 1 and 2
 | Trial 1 |  | Trial 2
 | Placebo | omalizumab | Placebo | omalizumab
Number of patients | 65 | 72 | 65 | 62
Nasal Polyp Score
Mean Baseline Score | 6.3 | 6.2 | 6.1 | 6.4
LS Mean Change From Baseline at Week 24 | 0.1 | -1.1 | -0.3 | -0.9
Difference in LS means vs. placebo | -1.1 |  | -0.6
95% CI for difference | -1.6, -0.7 |  | -1.1, -0.1
p-value | <0.0001 |  | 0.0140
7-day Average of Daily Nasal Congestion Score
Mean Baseline Score | 2.5 | 2.4 | 2.3 | 2.3
LS Mean Change From Baseline at Week 24 | -0.4 | -0.9 | -0.2 | -0.7
Difference in LS means vs. placebo | -0.6 |  | -0.5
95% CI for difference | -0.8, -0.3 |  | -0.8, -0.2
p-value | 0.0004 |  | 0.0017
CRSwNP= chronic rhinosinusitis with nasal polyps; LS=least-square. Change from baseline was analyzed using a mixed-effect model of repeated measures (MMRM) model with baseline score, baseline score/timepoint (week) interaction as covariates, and the following factors: geographic region, asthma/aspirin sensitivity comorbidity status, timepoint, treatment group, treatment/timepoint interaction.

The mean NPS and NCS at each study week by treatment group is shown in Figure 1.

Figure 1. Mean Change from Baseline in Nasal Congestion Score and Mean Change from Baseline in Nasal Polyp Score by Treatment Group in CRSwNP Trials 1 and 2

Omalizumab had statistically significant improvements on sense of smell score compared to placebo. Sense of smell was measured by a daily assessment on a 0 to 3 point severity scale (0=no symptoms, 1=mild symptoms, 2=moderate symptoms, 3=severe symptoms). The LS mean difference for change from baseline at Week 24 in sense of smell score in omalizumab compared to placebo was -0.3 (95% CI: -0.6, -0.1) in CRSwNP Trial 1 and -0.5 (95% CI: -0.7, -0.2) in CRSwNP Trial 2.

Omalizumab had statistically significant improvements on post-nasal drip compared to placebo. The LS mean difference for change from baseline at Week 24 in post-nasal drip score in omalizumab compared to placebo was -0.6 (95% CI: -0.8, -0.3) in CRSwNP Trial 1 and -0.5 (95% CI: -0.8, -0.3) in CRSwNP Trial 2.

Omalizumab had statistically significant improvements on runny nose compared to placebo. The LS mean difference for change from baseline at Week 24 in runny nose score in omalizumab compared to placebo was -0.4 (95% CI: -0.7, -0.2) in CRSwNP Trial 1 and -0.6 (95% CI: -0.9, -0.4) in CRSwNP Trial 2.

In a pre-specified pooled analysis of systemic corticosteroid use during the 24-week treatment period, there was no significant reduction in systemic corticosteroid use between the treatment arms. The proportion of patients taking systemic corticosteroid in omalizumab was 2.3% compared to 6.2% in placebo. The odds-ratio of systemic corticosteroid use with omalizumab compared to placebo was 0.4 (95% CI: 0.1, 1.5).

There were no sino-nasal surgeries reported, in either placebo or omalizumab arms, in either Trial.

14.3 IgE-Mediated Food Allergy

The safety and efficacy of omalizumab was evaluated in a multi-center, randomized, double-blind, placebo-controlled Food Allergy (FA) trial [NCT03881696] in 168 adult patients and pediatric patients 1 year of age to less than 56 years who were allergic to peanut and at least two other foods, including milk, egg, wheat, cashew, hazelnut, or walnut (i.e., studied foods). The FA trial enrolled patients who experienced dose-limiting symptoms (e.g., moderate to severe skin, respiratory or gastrointestinal symptoms) to a single dose of ≤100 mg of peanut protein and ≤300 mg protein for each of the other two foods (milk, egg, wheat, cashew, hazelnut, or walnut) during the screening double-blind placebo-controlled food challenge (DBPCFC). Patients with a history of severe anaphylaxis (defined as neurological compromise or requiring intubation) were excluded from the study. Patients were randomized 2:1 to receive a subcutaneous dosage of omalizumab or placebo based on serum total IgE level (IU/mL), measured before the start of treatment, and by body weight according to Table 4 [see Dosage and Administration (2.4)] for 16 to 20 weeks. After 16 to 20 weeks of treatment, each patient completed a DBPCFC consisting of placebo and each of their 3 studied foods. Following the DBPCFC, the first 60 patients that included 59 pediatric patients and one adult patient who completed the double-blind, placebo-controlled phase of the study could continue to receive omalizumab in a 24 to 28 week open-label extension.

Efficacy of omalizumab is based on 165 pediatric patients who were included in the efficacy analyses provided below. The mean age of the pediatric patients was 8 years (age range: 1 to 17 years); 37% were less than 6 years of age, 38% were 6 to less than 12 years of age, and 25% were 12 to less than 18 years of age. Patient population were 56% male, 63% White, 13% Asian, 7% Black, 16% Other, and 55% of patients had a history of asthma.

The primary efficacy endpoint was the percentage of patients who were able to consume a single dose of ≥600 mg of peanut protein without dose-limiting symptoms (e.g., moderate to severe skin, respiratory or gastrointestinal symptoms) during DBPCFC. Table 15 shows omalizumab treatment led to a statistically higher response rate (68%) than placebo (5%).

The secondary efficacy endpoints were the percentage of patients who were able to consume a single dose of ≥1000 mg of cashew, milk, or egg protein without dose-limiting symptoms during DBPCFC. The study met the secondary endpoints and demonstrated that omalizumab treatment led to statistically higher response rates than placebo for all three foods. See Table 15 for details.

Table 15. DBPCFC Response Rates in Pediatric Patients for Single Dose of Peanut, Cashew, Milk or Egg Protein in FA Trial
Food, Challenge Dose | Response Rate [Response defined as consumption of a single dose of the specified amount of food without dose-limiting symptoms.] (%) (n/N) |  | Treatment Difference (%) (Omalizumab-Placebo) (95% CI)
Food, Challenge Dose | Omalizumab | Placebo | Treatment Difference (%) (Omalizumab-Placebo) (95% CI)
Peanut, ≥600 mg | 68% (75/110) | 5% (3/55) | 63% (50%, 73%)
Peanut, ≥1000 mg [Consumption of a single dose of ≥1000 mg of peanut protein was an additional secondary endpoint. The key secondary efficacy endpoints were the percentage of patients who were able to consume a single dose of ≥1000 mg of cashew, milk, or egg protein.] | 65% (72/110) | 0% (0/55) | 65% (56%, 74%)
Cashew, ≥1000 mg | 42% (27/64) | 3% (1/30) | 39% (20%, 53%)
Milk, ≥1000 mg | 66% (25/38) | 11% (2/19) | 55% (29%, 73%)
Egg, ≥1000 mg | 67% (31/46) | 0% (0/19) | 67% (49%, 80%)
CI = Confidence interval; DBPCFC = Double-blind placebo-controlled food challenge; n = Number of responders;
N = Total number of patients receiving food, challenge dose.
Notes: Subjects without an exit DBPCFC or evaluable exit DBPCFC were counted as non-responders; P-values from two-sided Fisher's exact tests were <0.0001 for all the food challenge doses.

Seventeen percent of omalizumab treated patients were not able to consume >100 mg of peanut protein without moderate to severe dose-limiting symptoms. Eighteen, 22, and 41 percent of omalizumab-treated patients were not able to consume >300 mg of milk, egg, or cashew protein, respectively, without moderate to severe dose-limiting symptoms.

Additional secondary analyses included the percentage of patients who were able to consume at least two or all three foods during DBPCFC. For two foods, 71% of omalizumab treated patients were able to consume a single dose of ≥600 mg versus 5% in the placebo group and 67% were able to consume a single dose of ≥1000 mg versus 4% in the placebo group. For a single dose of ≥600 mg of three foods, the response rates were 48% in the omalizumab group versus 4% in the placebo group and for a single dose of ≥1000 mg of three foods, the response rate in the omalizumab group was 39% while none of the placebo patients were able to consume the challenge dose without symptoms.

The effectiveness of omalizumab in adults is supported by the adequate and well-controlled trial of omalizumab in pediatric patients, disease similarity in pediatric and adult patients, and pharmacokinetic (PK) similarity [see Clinical Pharmacology (12.3)].

While efficacy cannot be established from uncontrolled, open-label studies, for 38 pediatric patients who continued omalizumab for 24-28 weeks in an open-label extension, the percentage of patients who were able to consume ≥600 mg of peanut protein and ≥1000 mg of egg, milk, and/or cashew protein without moderate to severe dose-limiting symptoms was maintained.

14.4 Chronic Spontaneous Urticaria

Adult and Adolescent Patients 12 Years of Age and Older

The safety and efficacy of omalizumab for the treatment of chronic spontaneous urticaria (CSU), previously referred to as chronic idiopathic urticaria (CIU) was assessed in two placebo-controlled, multiple-dose clinical trials of 24 weeks' duration (CSU Trial 1; n= 319, [NCT01287117]) and 12 weeks' duration (CSU Trial 2; n=322, [NCT01292473]). Patients received omalizumab 75 mg, 150 mg, or 300 mg or placebo by SC injection every 4 weeks in addition to their baseline level of H1 antihistamine therapy for 24 or 12 weeks, followed by a 16-week washout observation period. A total of 640 patients (165 males, 475 females) were included for the efficacy analyses. Most patients were white (84%) and the median age was 42 years (range 12–72).]) and 12 weeks' duration (CSU Trial 2; n=322, [NCT01292473]). Patients received omalizumab 75 mg, 150 mg, or 300 mg or placebo by SC injection every 4 weeks in addition to their baseline level of H1 antihistamine therapy for 24 or 12 weeks, followed by a 16-week washout observation period. A total of 640 patients (165 males, 475 females) were included for the efficacy analyses. Most patients were white (84%) and the median age was 42 years (range 12–72).

Disease severity was measured by a weekly urticaria activity score (UAS7, range 0–42), which is a composite of the weekly itch severity score (range 0–21) and the weekly hive count score (range 0–21). All patients were required to have a UAS7 of ≥16, and a weekly itch severity score of ≥8 for the 7 days prior to randomization, despite having used an H1 antihistamine for at least 2 weeks.

The mean weekly itch severity scores at baseline were fairly balanced across treatment groups and ranged between 13.7 and 14.5 despite use of an H1 antihistamine at an approved dose. The reported median durations of CSU at enrollment across treatment groups were between 2.5 and 3.9 years (with an overall subject-level range of 0.5 to 66.4 years).

In both CSU Trials 1 and 2, patients who received omalizumab 150 mg or 300 mg had greater decreases from baseline in weekly itch severity scores and weekly hive count scores than placebo at Week 12. Representative results from CSU Trial 1 are shown (Table 16); similar results were observed in CSU Trial 2. The 75-mg dose did not demonstrate consistent evidence of efficacy and is not approved for use.

Table 16. Change from Baseline to Week 12 in Weekly Itch Severity Score and Weekly Hive Count Score in CSU Trial 1 [Modified intent-to-treat (mITT) population: all patients who were randomized and received at least one dose of study medication.]
 | Omalizumab 75 mg | Omalizumab 150 mg | Omalizumab 300 mg | Placebo
n | 77 | 80 | 81 | 80
Weekly Itch Severity Score
Mean Baseline Score (SD) | 14.5 (3.6) | 14.1 (3.8) | 14.2 (3.3) | 14.4 (3.5)
Mean Change Week 12 (SD) | −6.46 (6.14) | −6.66 (6.28) | −9.40 (5.73) | −3.63 (5.22)
Difference in LS means vs. placebo | −2.96 | −2.95 | −5.80
95% CI for difference | −4.71, −1.21 | −4.72, −1.18 | −7.49, −4.10 | -
Weekly Hive Count Score [Score measured on a range of 0–21]
Mean Baseline Score (SD) | 17.2 (4.2) | 16.2 (4.6) | 17.1 (3.8) | 16.7 (4.4)
Mean Change Week 12 (SD) | −7.36 (7.52) | −7.78 (7.08) | −11.35 (7.25) | −4.37 (6.60)
Difference in LS means vs. placebo | −2.75 | −3.44 | −6.93
95% CI for difference | −4.95, −0.54 | −5.57, −1.32 | −9.10, −4.76 | -

The mean weekly itch severity score at each study week by treatment groups is shown in Figure 2. Representative results from CSU Trial 1 are shown; similar results were observed in CSU Trial 2. The appropriate duration of therapy for CSU with omalizumab has not been determined.

Figure 2. Mean Weekly Itch Severity Score by Treatment Group Modified Intent to Treat Patients in CSU Trial 1

In CSU Trial 1, a larger proportion of patients treated with omalizumab 300 mg (36%) reported no itch and no hives (UAS7=0) at Week 12 compared to patients treated with omalizumab 150 mg (15%), omalizumab 75 mg (12%), and placebo group (9%). Similar results were observed in CSU Trial 2.

16 HOW SUPPLIED/STORAGE AND HANDLING

Injection (Prefilled Syringe)

Omalizumab-igec injection is a clear to opalescent and colorless to pale brownish-yellow solution for subcutaneous use.

Omalizumab-igec injection is provided in a single-dose prefilled glass syringe with a 27-gauge special thin wall needle. The syringe plunger stopper and needle cap are not made with natural rubber latex.

Omalizumab-igec is available as prefilled syringe as described in Table 17.

Table 17. Omalizumab-igec Prefilled Syringe Strengths and Package Configurations
Package Configuration | Strength | NDC | Syringe Counts
1 prefilled syringe with a 27-gauge staked needle syringe with a yellow plunger rod | 75 mg/ 0.5 mL | 72606-052-01 | 1
1 prefilled syringe with a 27-gauge staked needle syringe with a blue plunger rod | 150 mg/mL | 72606-053-01 | 1
1 prefilled syringe with a 27-gauge staked needle syringe with a white plunger rod | 300 mg/2 mL (150 mg/mL) | 72606-061-01 | 1
2 prefilled syringes with a 27-gauge staked needle syringe with a white plunger rod | 300 mg/2 mL (150 mg/mL) | 72606-061-02 | 2 (2 × 1) (multipack)
The Omalizumab-igec prefilled syringe is not made with natural rubber.

Storage

Omalizumab-igec prefilled syringe should be shipped and stored under refrigerated conditions 36°F to 46°F (2°C to 8°C) in the original carton. Protect from direct sunlight. Omalizumab-igec prefilled syringe can be removed from and placed back in the refrigerator if needed. The total combined time out of the refrigerator may not be more than 7 days. Do not use if prefilled syringe is left at temperatures above 77°F (25°C).

Do not freeze. Do not use if the prefilled syringe has been frozen. Do not shake.

17 PATIENT COUNSELING INFORMATION

Advise the patient to read the FDA-approved patient labeling (Medication Guide and Instructions for Use).

Anaphylaxis

Inform patients of the risk of life-threatening anaphylaxis with Omalizumab-igec including the following points [see Boxed Warning and Warnings and Precautions (5.1)]:

- There have been reports of anaphylaxis occurring up to 4 days after administration of omalizumab products
- Initiate Omalizumab-igec only in a healthcare setting by healthcare providers
- Observe patients closely following administration
- Inform patients of the signs and symptoms of anaphylaxis
- Instruct patients to seek immediate medical care should such signs or symptoms occur

Potential Medication Error Related to Emergency Treatment of Anaphylaxis

Advise patients, parents, or caregivers that Omalizumab-igec should not be used for the emergency treatment of allergic reactions, including anaphylaxis [see Warnings and Precautions (5.9)].

Continuation of Other Medications

Instruct patients receiving Omalizumab-igec not to decrease the dose of, or stop taking any other asthma, CRSwNP, CSU or IgE-mediated food allergy medications or allergen immunotherapy unless otherwise instructed by their physician. Inform patients that they may not see immediate improvement in their asthma, CRSwNP, CSU or IgE-mediated food allergy symptoms after beginning Omalizumab-igec therapy.

Instruction on Injection Technique

If a patient or caregiver is to administer subcutaneous Omalizumab-igec prefilled syringe, instruct on injection technique and assess ability to inject subcutaneously to ensure proper administration of Omalizumab-igec. For patients who require more than 1 injection to complete their prescribed dose, instruct patients to administer all injections consecutively and in one sitting [See Dosage and Administration (2.7), Warnings and Precautions (5.1), and Instructions for Use].

Manufactured by:
CELLTRION, Inc.
23, Academy-ro, Yeonsu-gu,
Incheon, 22014,
Republic of Korea
U.S. License Number: 1996

Distributed by:
CELLTRION USA, Inc.
1 Evertrust Plaza Suite 1207,
Jersey City, NJ, 07302

Revised Date: 12/2025

MEDICATION GUIDE
Omalizumab-igec (oh mah lye zoo' mab)
injection, for subcutaneous use

What is the most important information I should know about Omalizumab-igec?
Omalizumab-igec may cause serious side effects, including:
Severe allergic reaction. A severe allergic reaction called anaphylaxis can happen when you receive Omalizumab-igec. The reaction can occur after the first dose, or after many doses. It may also occur right after a Omalizumab-igec injection or days later. Anaphylaxis is a life-threatening condition and can lead to death. Go to the nearest emergency room right away if you have any of these symptoms of an allergic reaction:

- wheezing, shortness of breath, cough, chest tightness, or trouble breathing
- low blood pressure, dizziness, fainting, rapid or weak heartbeat, anxiety, or feeling of "impending doom"
- flushing, itching, hives, or feeling warm
- swelling of the throat or tongue, throat tightness, hoarse voice, or trouble swallowing

Your healthcare provider will monitor you closely for symptoms of an allergic reaction while you are receiving Omalizumab-igec and for a period of time after treatment is initiated. Your healthcare provider should talk to you about getting medical treatment if you have symptoms of an allergic reaction.

What is Omalizumab-igec?
Omalizumab-igec is an injectable prescription medicine used to treat:

- moderate to severe persistent asthma in people 6 years of age and older whose asthma symptoms are not well controlled with asthma medicines called inhaled corticosteroids. A skin or blood test is performed to see if you have allergies to year-round allergens. It is not known if Omalizumab-igec is safe and effective in people with asthma under 6 years of age.
- chronic rhinosinusitis with nasal polyps (CRSwNP) in people 18 years of age and older when medicines to treat CRSwNP called nasal corticosteroids have not worked well enough. It is not known if Omalizumab-igec is safe and effective in people with CRSwNP under 18 years of age.
- food allergy in people 1 year of age and older to reduce allergic reactions that may occur after accidentally eating one or more foods to which you are allergic. While taking Omalizumab-igec you should continue to avoid all foods to which you are allergic. It is not known if Omalizumab-igec is safe and effective in people with food allergy under 1 year of age.
- chronic spontaneous urticaria (CSU, previously referred to as chronic idiopathic urticaria (CIU), chronic hives without a known cause) in people 12 years of age and older who continue to have hives that are not controlled with H1 antihistamine treatment. It is not known if Omalizumab-igec is safe and effective in people with CSU under 12 years of age.

Omalizumab-igec should not be used for the emergency treatment of any allergic reactions, including anaphylaxis.
Omalizumab-igec should also not be used to treat other forms of hives, or sudden breathing problems.

Who should not receive and use Omalizumab-igec?
Do not receive and use Omalizumab-igec if you:

- are allergic to omalizumab products or any of the ingredients in Omalizumab-igec. See the end of this Medication Guide for a complete list of ingredients in Omalizumab-igec.

What should I tell my healthcare provider before receiving Omalizumab-igec?
Before receiving Omalizumab-igec, tell your healthcare provider about all of your medical conditions, including if you:

- have sudden breathing problems (bronchospasm).
- have ever had a severe allergic reaction called anaphylaxis.
- have or have had a parasitic infection.
- have or have had cancer.
- are pregnant or plan to become pregnant. It is not known if Omalizumab-igec may harm your unborn baby.
- are breastfeeding or plan to breastfeed. It is not known if Omalizumab-igec passes into your breast milk. Talk with your healthcare provider about the best way to feed your baby while you receive and use Omalizumab-igec.

Tell your healthcare provider about all the medicines you take, including prescription and over-the-counter medicines, vitamins, and herbal supplements.

How should I receive and use Omalizumab-igec?

- When starting treatment Omalizumab-igec should be given by your healthcare provider in a healthcare setting.
- If your healthcare provider decides that you or a caregiver may be able to give your own Omalizumab-igec prefilled syringe injections, you should receive training on the right way to prepare and inject Omalizumab-igec.
- Do not try to inject Omalizumab-igec until you have been shown the right way to give Omalizumab-igec prefilled syringe injections by a healthcare provider. Use Omalizumab-igec exactly as prescribed by your healthcare provider.
- For children 12 years of age and older, Omalizumab-igec prefilled syringe may be self-injected under adult supervision. For children 1 to 11 years of age, Omalizumab-igec prefilled syringe should be injected by a caregiver.
- See the detailed Instructions for Use that comes with Omalizumab-igec for information on the right way to prepare and inject Omalizumab-igec.
- Omalizumab-igec is given in 1 or more injections under the skin (subcutaneous), 1 time every 2 or 4 weeks.
- In people with asthma, CRSwNP and food allergy, a blood test for a substance called IgE must be performed before starting Omalizumab-igec to determine the appropriate dose and dosing frequency.
- In people with chronic hives, a blood test is not necessary to determine the dose or dosing frequency.
- Do not decrease or stop taking any of your other asthma, CRSwNP, hive medicine, food allergy medicine or allergen immunotherapy unless your healthcare providers tell you to.
- You may not see improvement in your symptoms right away after Omalizumab-igec treatment. If your symptoms do not improve or get worse, call your healthcare provider.
- If you inject more Omalizumab-igec than prescribed, call your healthcare provider right away.

What are the possible side effects of Omalizumab-igec?
Omalizumab-igec may cause serious side effects, including:

- See "What is the most important information I should know about Omalizumab-igec?"
- Cancer. Cases of cancer were observed in some people who received Omalizumab-igec.
- Inflammation of your blood vessels. Rarely, this can happen in people with asthma who receive Omalizumab-igec. This usually, but not always, happens in people who also take a steroid medicine by mouth that is being stopped or the dose is being lowered. It is not known whether this is caused by Omalizumab-igec. Tell your healthcare provider right away if you have:

- rash
- shortness of breath

- chest pain
- a feeling of pins and needles or numbness of your arms or legs

- Fever, muscle aches, and rash. Some people get these symptoms 1 to 5 days after receiving a Omalizumab-igec injection. If you have any of these symptoms, tell your healthcare provider.
- Parasitic infection. Some people who are at a high risk for parasite (worm) infections, get a parasite infection after receiving Omalizumab-igec. Your healthcare provider can test your stool to check if you have a parasite infection.
- Heart and circulation problems. Some people who receive Omalizumab-igec have had chest pain, heart attack, blood clots in the lungs or legs, or temporary symptoms of weakness on one side of the body, slurred speech, or altered vision. It is not known whether these are caused by Omalizumab-igec.

The most common side effects of Omalizumab-igec:

- In adults and children 12 years of age and older with asthma: joint pain especially in your arms and legs, dizziness, feeling tired, itching, skin rash, bone fractures, and pain or discomfort of your ears.
- In children 6 to less than 12 years of age with asthma: swelling of the inside of your nose, throat, or sinuses, headache, fever, throat infection, ear infection, abdominal pain, stomach infection, and nose bleeds.
- In adults with chronic rhinosinusitis with nasal polyps: headache, injection site reactions, joint pain, upper abdominal pain, and dizziness.
- In people with chronic spontaneous urticaria: nausea, headaches, swelling of the inside of your nose, throat or sinuses, cough, joint pain, and upper respiratory tract infection.
- In people with food allergy: injection site reactions and fever.

These are not all the possible side effects of Omalizumab-igec. Call your doctor for medical advice about side effects. You may report side effects to FDA at 1-800-FDA-1088.

How should I store Omalizumab-igec?

- Store Omalizumab-igec in the refrigerator between 36°F to 46°F (2°C to 8°C).
- Keep your unused Omalizumab-igec prefilled syringes in the original carton until use to protect them from light.
- Omalizumab-igec prefilled syringe can be removed from and placed back in the refrigerator if needed. The total combined time out of refrigerator may not be more than 7 days. Do not use if Omalizumab-igec prefilled syringe is left at temperatures above 77°F (25°C) and discard in a FDA-cleared sharps disposal container.
- Do not freeze. Do not use if Omalizumab-igec prefilled syringes have been frozen.
- Do not shake.
- Keep Omalizumab-igec out of direct sunlight.
- Do not use Omalizumab-igec past the expiration date.

Keep the Omalizumab-igec prefilled syringe, FDA-cleared sharps disposal container and all medicines out of the reach of children.

General information about the safe and effective use of Omalizumab-igec.
Medicines are sometimes prescribed for purposes other than those listed in a Medication Guide. Do not use Omalizumab-igec for a condition for which it was not prescribed. Do not give Omalizumab-igec to other people, even if they have the same symptoms that you have. It may harm them. You can ask your pharmacist or healthcare provider for information about Omalizumab-igec that is written for health professionals.
For more information, call 800-560-9414

What are the ingredients in Omalizumab-igec?
Active ingredient: omalizumab-igec
Inactive ingredients:
Prefilled syringe : arginine hydrochloride, histidine, L-histidine hydrochloride monohydrate, and polysorbate 20
Manufactured by: CELLTRION, Inc. 23, Academy-ro, Yeonsu-gu, Incheon, 22014, Republic of Korea, U.S. License No.: 1996Distributed by: CELLTRION USA, Inc. One Evertrust Plaza Suite 1207, Jersey City, NJ, 07302

This Medication Guide has been approved by the U.S. Food and Drug Administration

Revised: 12/2025

INSTRUCTIONS FOR USE
Omalizumab-igec (oh mah lye zoo' mab)
injection, for subcutaneous use
Single-Dose Prefilled Syringe

Read and follow the Instructions for Use that come with your Omalizumab-igec Prefilled Syringe before you start using it and each time you get a refill. There may be new information. Before you use Omalizumab-igec Preﬁlled Syringe for the ﬁrst time, make sure your healthcare provider shows you the right way to use it.

Do not use Omalizumab-igec for the emergency treatment of any allergic reactions, including anaphylaxis, hives or sudden breathing problems.

For children 12 years of age and older, Omalizumab-igec Prefilled Syringe may be self-injected under adult supervision.

For children 1 to 11 years of age, Omalizumab-igec Prefilled Syringe should be injected by a caregiver and healthcare provider.

Parts of the Prefilled Syringe (see Figure A)

Figure A

Choose the Correct Prefilled Syringe or Combination of Prefilled Syringes

Omalizumab-igec Prefilled Syringes are available in 3 dose strengths (see Figure B). These instructions are to be used for all dose strengths.

Figure B

Your prescribed dose may require more than 1 injection. The Dosing Table (Figure C) below shows the combination of Prefilled Syringes needed to give your full dose. Check the label on the Omalizumab-igec carton to make sure you have received the correct Prefilled Syringe or combination of Prefilled Syringes for your prescribed dose. If your dose requires more than 1 injection, complete all injections for your prescribed dose, immediately one after another. Contact your healthcare provider if you have any questions.

Dosing Table

Note: Your healthcare provider may prescribe a different combination of Prefilled Syringes for your complete dose.

How Should I Store Omalizumab-igec?

- Store the unused Prefilled Syringe in the original carton and store the carton in a refrigerator between 36°F to 46°F (2°C to 8°C).
- Do not remove the Prefilled Syringe from its original carton during storage.
- Keep the Prefilled Syringe out of direct light.
- Do not freeze.
- Do not use if the Prefilled Syringe has been frozen.
- Before giving an injection, the carton can be removed from and placed back in the refrigerator if needed. The total combined time out of the refrigerator may not exceed 7 days. If the Prefilled Syringe is exposed to temperatures above 77°F (25°C), do not use it and throw away in a FDA-cleared sharps disposal container.
- Keep the Prefilled Syringe, and all medicines out of reach of children. Prefilled Syringe contains small parts.

Important information

- Do not open the sealed carton until you are ready to inject the Prefilled Syringe.
- Do not use if the carton or the Prefilled Syringe is damaged or appears to be tampered with.
- Do not take the Cap off until you are ready to inject the Prefilled Syringe.
- Do not use if the Prefilled Syringe has been dropped on a hard surface or dropped after removing the Cap.
- Do not reuse the same Prefilled Syringe.
- Do not leave the Prefilled Syringe unattended.
- Do not try to take the Prefilled Syringe apart at any time

Preparing for the Injection
1. Take the carton containing the Prefilled Syringe out of the refrigerator.
1a. If you need more than 1 Prefilled Syringe to deliver your prescribed dose (see Figure C), take all the cartons out of the refrigerator at the same time (each carton contains 1 Prefilled Syringe). The following steps must be followed for each Prefilled Syringe.

Figure D

2.Gather the supplies needed to give your injection. (see Figure D).-Carton containing Prefilled SyringeNot included in the carton:-Alcohol swab-Cotton ball or gauze-Adhesive bandage-FDA-cleared Sharps disposal containerNote: You may need more than 1 Prefilled Syringe for your prescribed dose. See the Dosing Table (Figure C) above for more information. Each carton contains 1 Prefilled Syringe.

Figure E

3.Check the expiration on the carton (see Figure E).

- Do not use it if the expiration date has passed.
- If the expiration date has passed, safely dispose of the carton in a FDA-cleared sharps disposal container (see Step 17. Dispose of the Prefilled Syringe) and contact your healthcare provider.

Figure F

4.Allow the Prefilled Syringe to reach room temperature.4a.Set aside the unopened carton on a clean, flat surface for at least 30 to 45 minutes to allow it to warm up. Leave the Prefilled Syringe in the carton to protect it from light (see Figure F).

- Do not warm the Prefilled Syringe using heat sources such as hot water or a microwave.
- If the Prefilled Syringe does not reach room temperature, this could cause the injection to feel uncomfortable and make it hard to push the Plunger rod.

Figure G

5.Wash your hands.5a.Wash your hands with soap and water and dry them thoroughly (see Figure G).

Figure H

6.Remove the Prefilled Syringe from the carton.6a.Open the carton.6b.Gripping from the syringe body lift the Prefilled Syringe from the carton (see Figure H).

- Do not touch the Plunger rod or Cap when removing the Prefilled Syringe from the carton.
- Do not flip the carton upside down to take out the Prefilled Syringe.

Figure I

7.Inspect the Prefilled Syringe.7a.Look at the Prefilled Syringe and make sure you have the correct medicine (Omalizumab-igec) and dosage.7b.Look at the Prefilled Syringe and make sure it is not cracked, damaged, or has been tampered with.•Do not use if the Prefilled Syringe is cracked, damaged, or appears to be tampered with.7c.Check the expiration date on the label of the Prefilled Syringe (see Figure I).

- Do not use if the expiration date has passed.

Note: If the expiration date is not visible in the viewing window, rotate the plunger rod of the Prefilled Syringe until the expiration date becomes visible.

Figure J

8.Inspect the Medicine.8a. Look at the Medicine and confirm that the liquid is clear to slightly cloudy, colorless to pale brownish-yellow, and free of particles (see Figure J).

- Do not use the Prefilled Syringe if the liquid is discolored, distinctly cloudy, or contains particles in it.
- You may see air bubbles in the liquid. This is normal.
- Do not try to remove the air bubbles.

8b.If the Medicine does not look as described or if the expiration date has passed, safely dispose of the Prefilled Syringe in a FDA-cleared sharps disposal container (see Step 17) and contact your healthcare provider.

Figure K

9.Choose an injection site (see Figure K)9a.If you are giving yourself the injection, you can inject into:-The front of the thighs.-The stomach area (abdomen) except within the 2-inch (5-cm) area around your belly button (navel).9b.If a caregiver or Health Care Provider (HCP) is giving the injection, they can use:-The outer area of the upper arm.-The front of the thighs.-The stomach area (abdomen) except within the 2-inch (5-cm) area around your belly button (navel).•Do not inject into moles, scars, bruises, or areas where the skin is tender, red, hard, or if there are breaks in the skin.•Do not inject through clothing. The injection site should be exposed, clean skin.9c.If your prescribed dose requires more than 1 injection, make sure your injections are at least 1 inch (2.5 cm) apart from each other.

Figure L

10.Clean the injection site.10a. Clean the injection site with an alcohol swab using a circular motion (see Figure L).10b. Let the skin dry for 10 seconds before injecting.

- Do not fan or blow on the clean area.
- Do not touch the injection site again before giving the injection.

Giving the Injection

Figure M

11.Remove the Cap.11a. Hold the Prefilled Syringe by the syringe body in one hand. 11.bGently pull the Cap straight off with the other hand (See Figure M).

- Do not remove the Cap until you are ready to inject.
- Do not twist the Cap.
- Do not hold, push or pull the Plunger rod while removing the Cap.
- You may see a few drops of liquid at the tip of the Needle. This is normal.

11c. Dispose of the Cap right away in a FDA-cleared sharps disposal container (see Step 17. Dispose of the Prefilled Syringe and Figure M).

- Do not re-cap the Prefilled Syringe.
- Do not touch the Needle or let it touch any surfaces after removing the Cap.

Figure N

12.Insert the Prefilled Syringe into the injection site.12a. Gently pinch a fold of skin at the injection site with one hand. Hold the pinched skin tightly until the injection is complete.Note: Pinching the skin is important to make sure that you inject under the skin (into the fatty area) but not any deeper (into muscle).12b. With a quick and "dart-like" motion, insert the Needle all the way into the pinched skin at an angle of about 45-degrees (see Figure N).Note:It is important to use the correct angle to make sure the Medicine is delivered under the skin (into the fatty area), or the injection could be uncomfortable and the Medicine may not work.

- Do not touch the Plunger rod while inserting the Needle into the skin.
- Do not insert the needle through clothing.
- Hold the Prefilled syringe tightly in place and do not change the angle of injection or insert the Needle again. Do not move and should avoid sudden movements throughout the injection.

Figure O

13.Give the injection.13a. Slowly push the Plunger rod all the way down until the full dose of medicine gets injected, and the syringe is empty (see Figure O).

- Do not change the position of the Prefilled Syringe after the injection has started.
- If the Plunger rod is not fully pressed, the Safety Guard will not extend to cover the Needle when it is removed.

Figure P

14.Remove the Prefilled Syringe from the injection site.14a. After the Prefilled Syringe is empty, slowly lift your thumb from the Plunger rod until the Needle is completely covered by the Safety Guard (see Figure P).

- If the Needle is not covered, carefully remove the Prefilled Syringe from the skin and dispose of the Prefilled Syringe in a FDA-cleared sharps disposal container (see Step 17. Dispose of the Prefilled Syringe).

14b. Remove the Prefilled Syringe from the injection site and release the pinch.

- Some bleeding may occur (see Step 15. Care for the injection site).
- Do not reuse the Prefilled Syringe.

15.Care for the injection site.15a. If some bleeding occurs or there is a drop of liquid at the injection site, treat the injection site by gently pressing, not rubbing, a cotton ball or gauze to the site and apply an adhesive bandage if needed.

- Do not rub the injection site.

15b. In case of skin contact with Medicine, wash the area that touched the Medicine with water.

16.If your prescribed dose requires more than 1 injection: 16a. Throw away the used Prefilled Syringe as described in Step 17. Dispose of the Prefilled Syringe .16b. Repeat Step 2 through Step 15for the next injection using a new Prefilled Syringe.

- Make sure each injection is at least 1 inch (2.5 cm) apart from each other.
- Complete all the required injections for your prescribed dose, immediately one after another.
- Contact your healthcare provider if you have any questions.

After the injection

Figure Q

17.Dispose of the Prefilled Syringe.17a. Put the used Prefilled Syringe in a FDA-cleared sharps disposal container right away after use (see Figure Q).

- The Omalizumab-igec Prefilled Syringe is a single dose syringe and should not be used again.
- Do not re-cap the Prefilled Syringe.
- Do not throw away (dispose of) the Prefilled Syringe in your household trash

If you do not have an FDA-cleared sharps disposal container, you may use a household container that is:-made of a heavy-duty plastic,-can be closed with a tight fitting, puncture-resistant lid, without sharps being able to come out,-upright and stable during use,-leak-resistant, and-properly labeled to warn of hazardous waste inside the containerWhen your sharps disposal container is almost full, you will need to follow your community guidelines for the right way to dispose of it. There may be state or local laws about how you should throw away used needles and syringes. For more information about safe sharps disposal, and for specific information about sharps disposal in the state that you live in, go to the FDA's website at: http://www.fda.gov/safesharpsdisposal.

- Do not dispose of your used sharps disposal container in your household trash unless your community guidelines permit this.
- Do not recycle your used sharps disposal container.

This Instructions for Use has been approved by the U.S. Food and Drug Administration

12/2025

Manufactured by:
CELLTRION, Inc. 23 Academy-ro, Yeonsu-gu, Incheon, 22014, Republic of Korea, U.S. License No.: 1996

PRINCIPAL DISPLAY PANEL - 75 mg/0.5 mL Syringe Carton

Rx only
NDC 72606-052-01

Omalizumab-igec
Injection

75 mg/0.5 mL

x 1

FOR SUBCUTANEOUS USE
ATTENTION: Dispense the enclosed
Medication Guide to each patient

1
single-dose
Prefilled Syringe with safety guard

Do not use for emergency treatment.

Your dose may require more than 1 injection. For questions, contact your healthcare provider.

CELLTRION USA
CELLTRION

PRINCIPAL DISPLAY PANEL - 150 mg/mL Syringe Carton

Rx only
NDC 72606-053-01

Omalizumab-igec
Injection

150 mg/mL

x 1

FOR SUBCUTANEOUS USE
ATTENTION: Dispense the enclosed
Medication Guide to each patient

1
single-dose
Prefilled Syringe with safety guard

Do not use for emergency treatment.

Your dose may require more than 1 injection. For questions, contact your healthcare provider.

CELLTRION USA
CELLTRION

PRINCIPAL DISPLAY PANEL - 300 mg/2 mL Syringe Carton

Rx only
NDC 72606-061-01

Omalizumab-igec
Injection

300 mg/2 mL (150 mg/mL)

x 1

FOR SUBCUTANEOUS USE
ATTENTION: Dispense the enclosed
Medication Guide to each patient

1
single-dose
Prefilled Syringe with safety guard

Do not use for emergency treatment.

Your dose may require more than 1 injection. For questions, contact your healthcare provider.

CELLTRION USA
CELLTRION